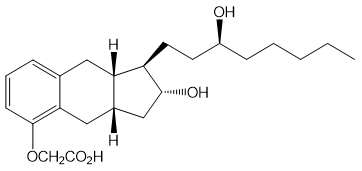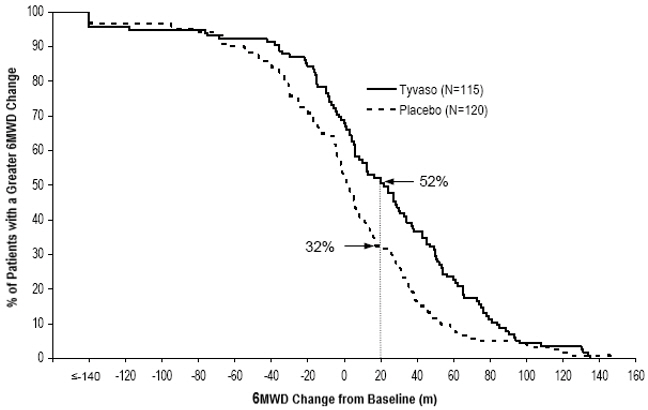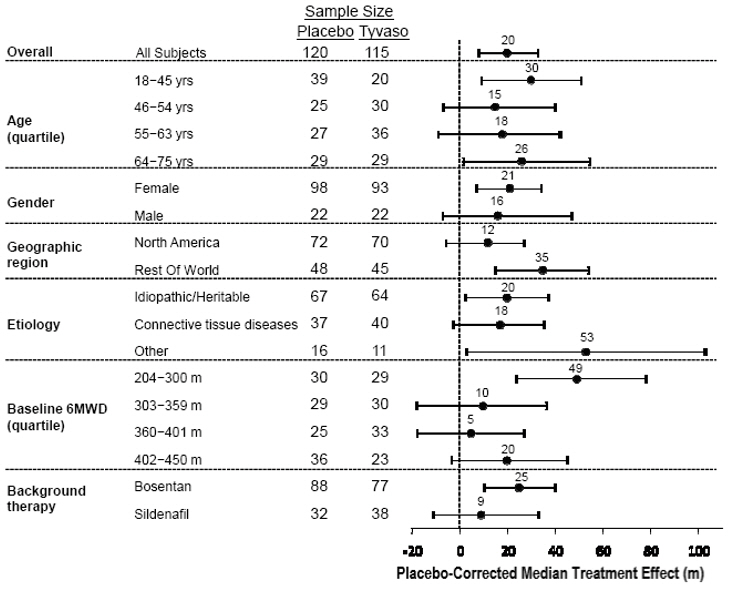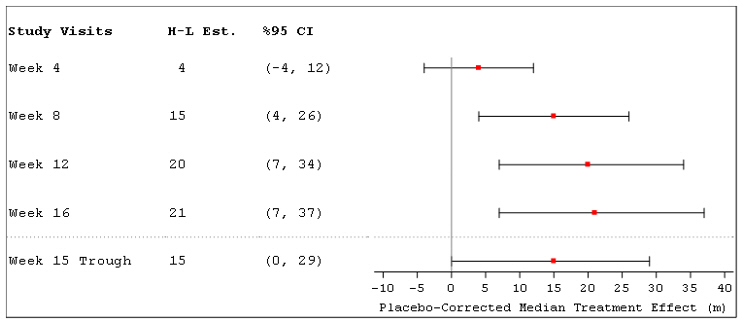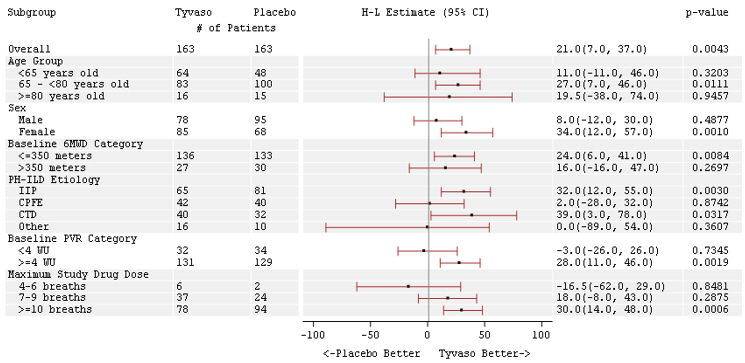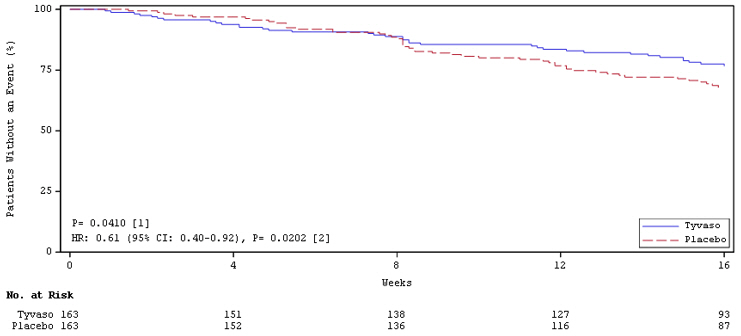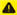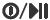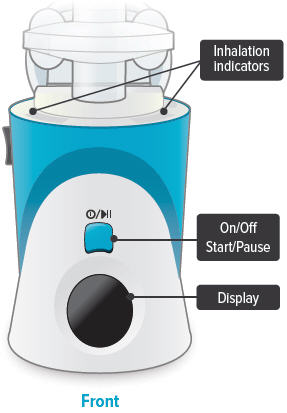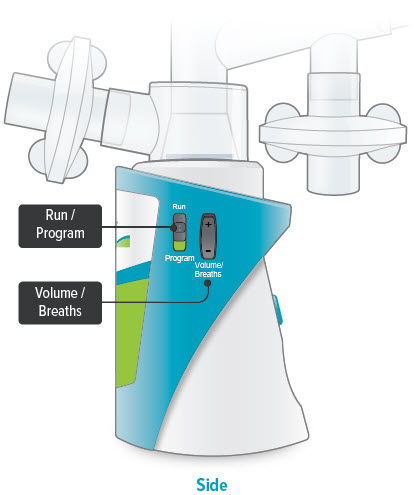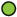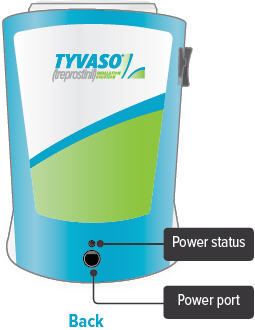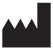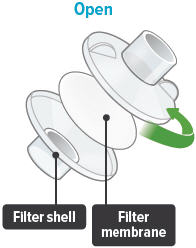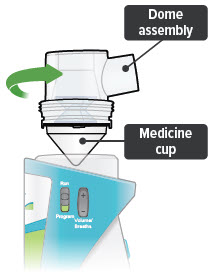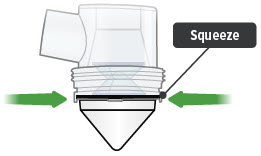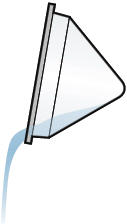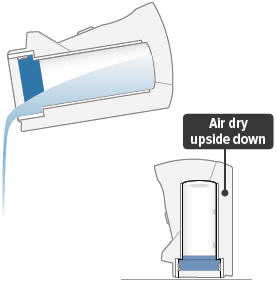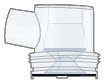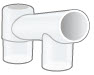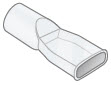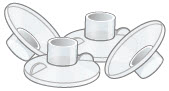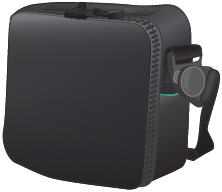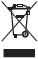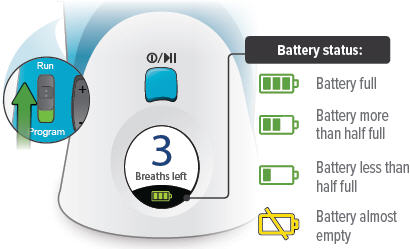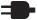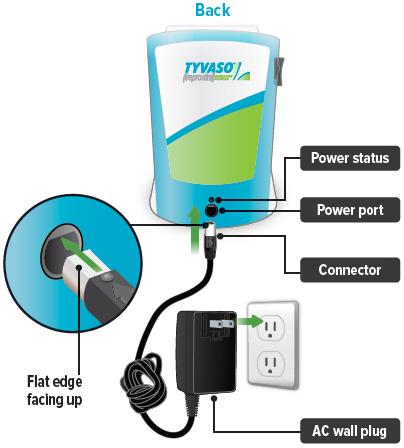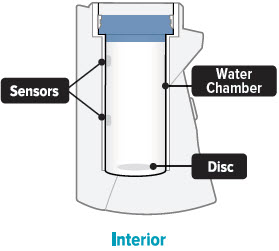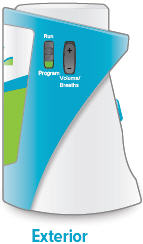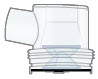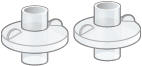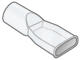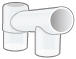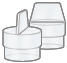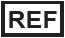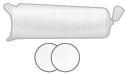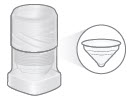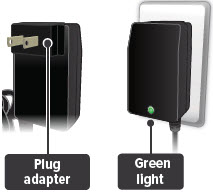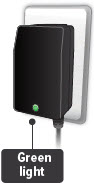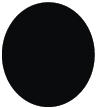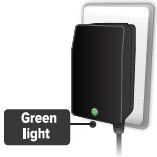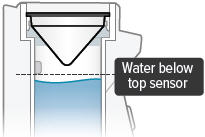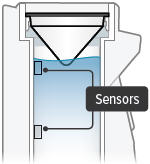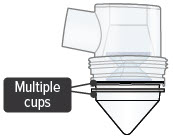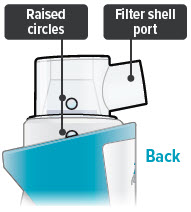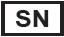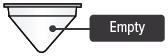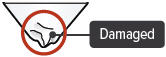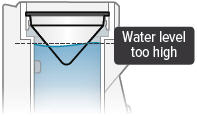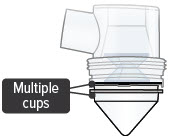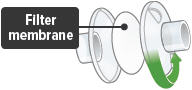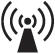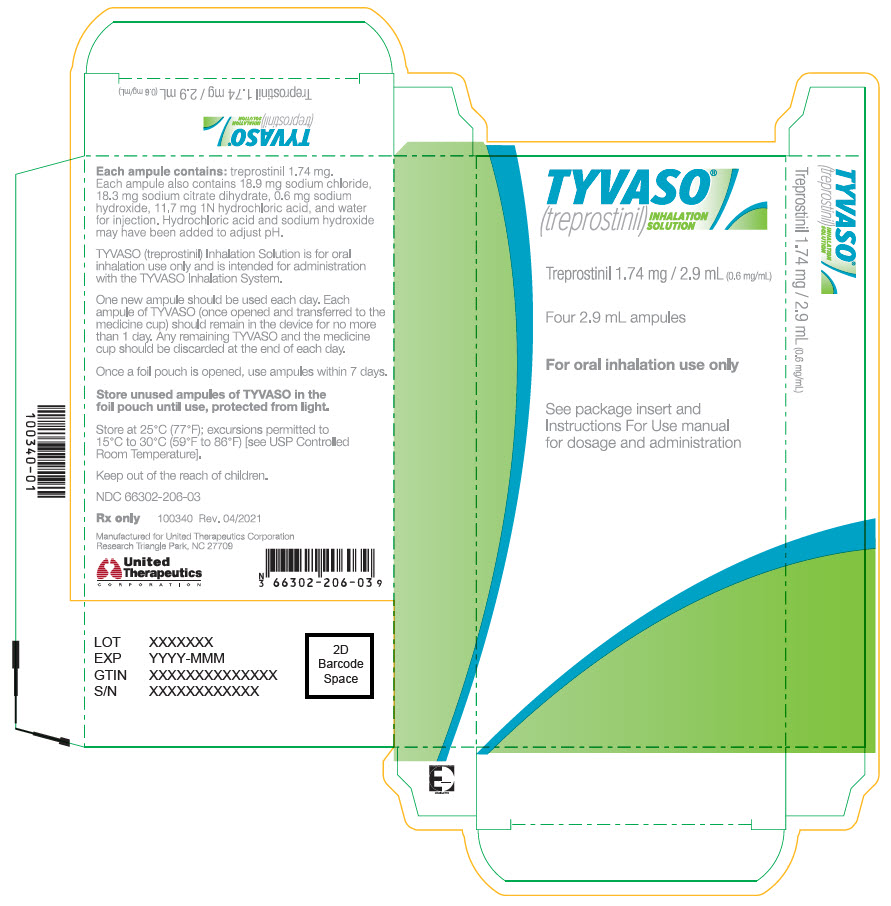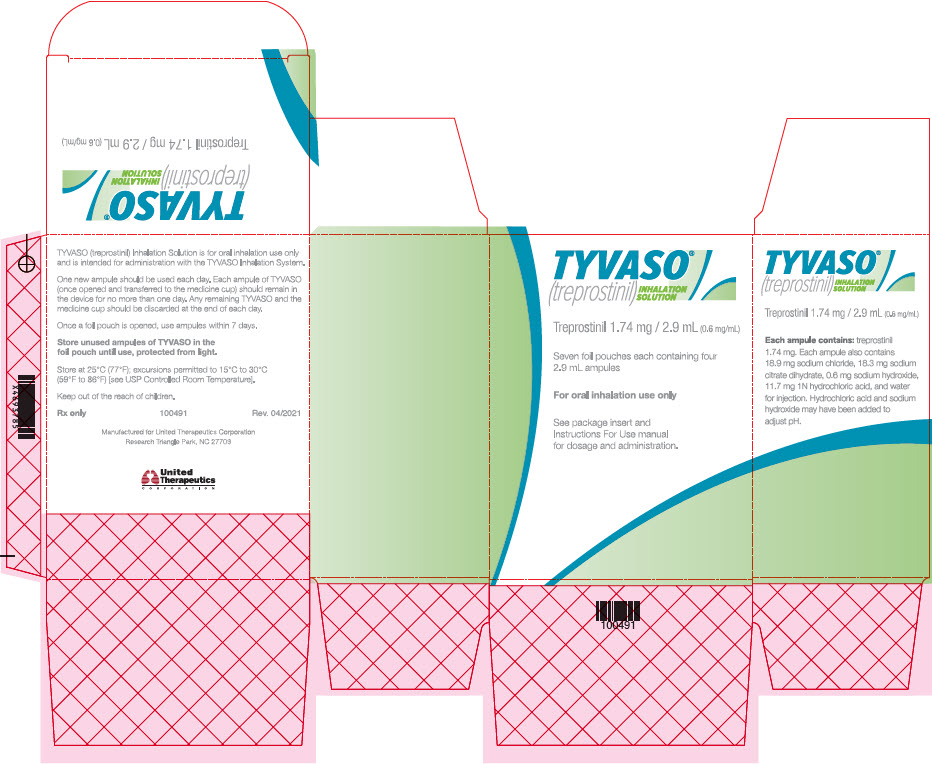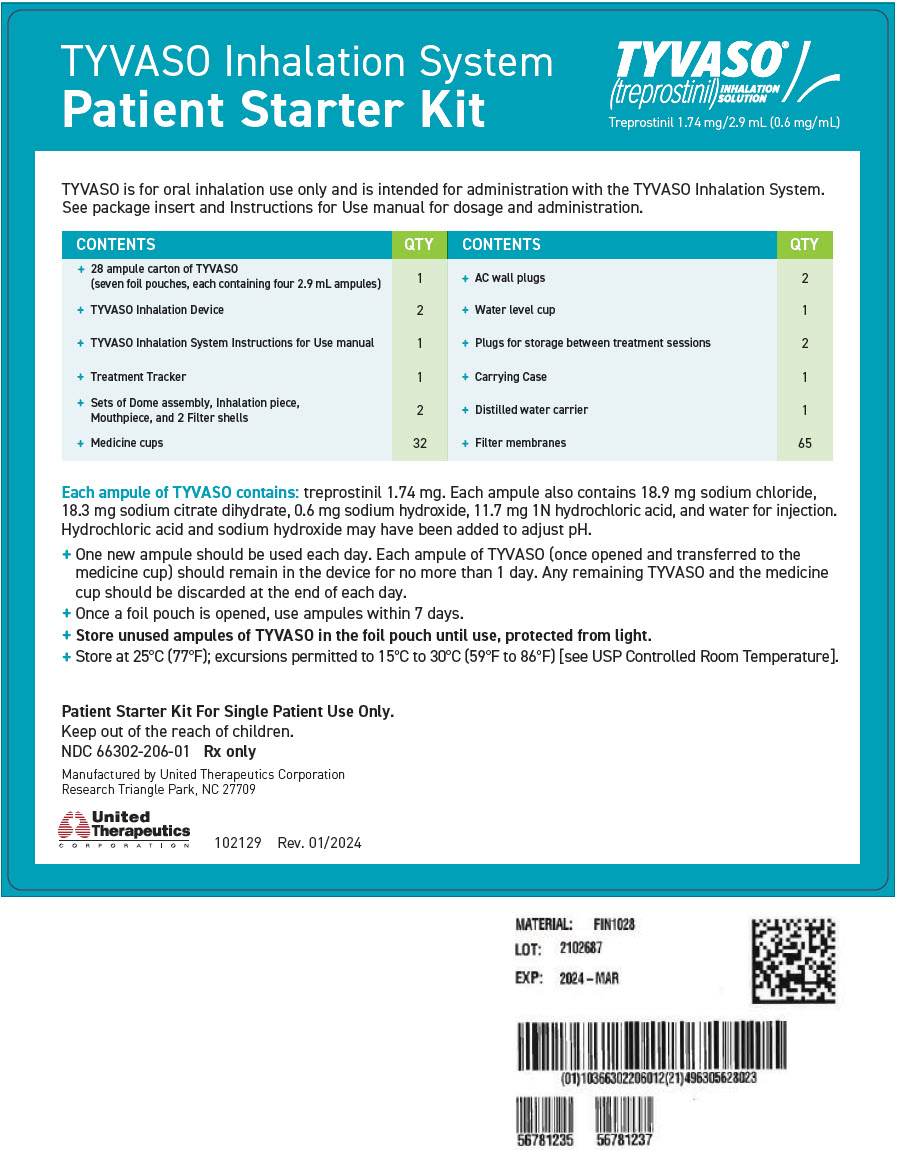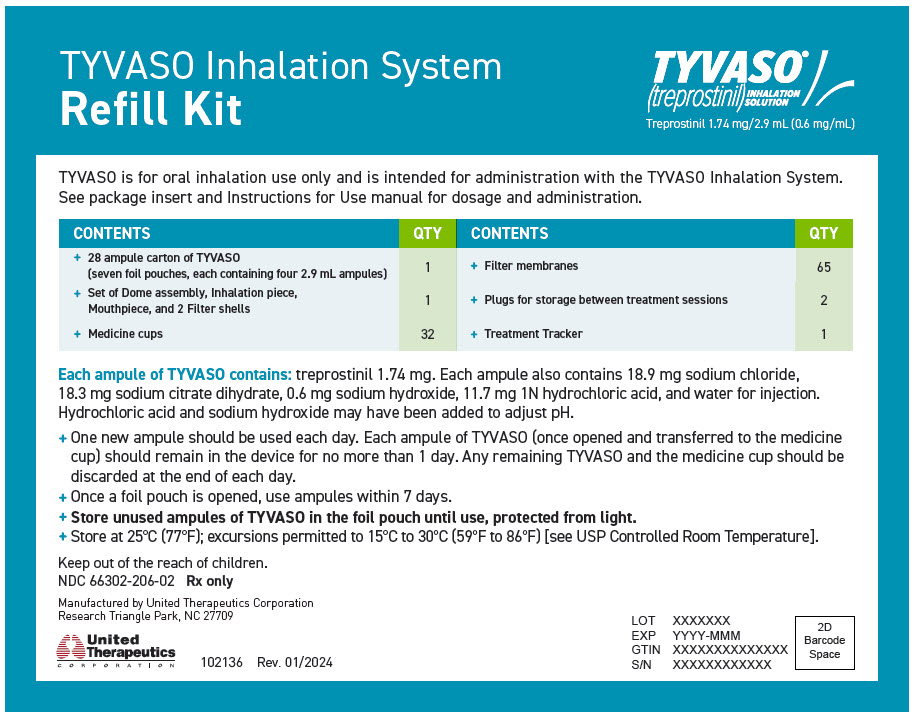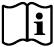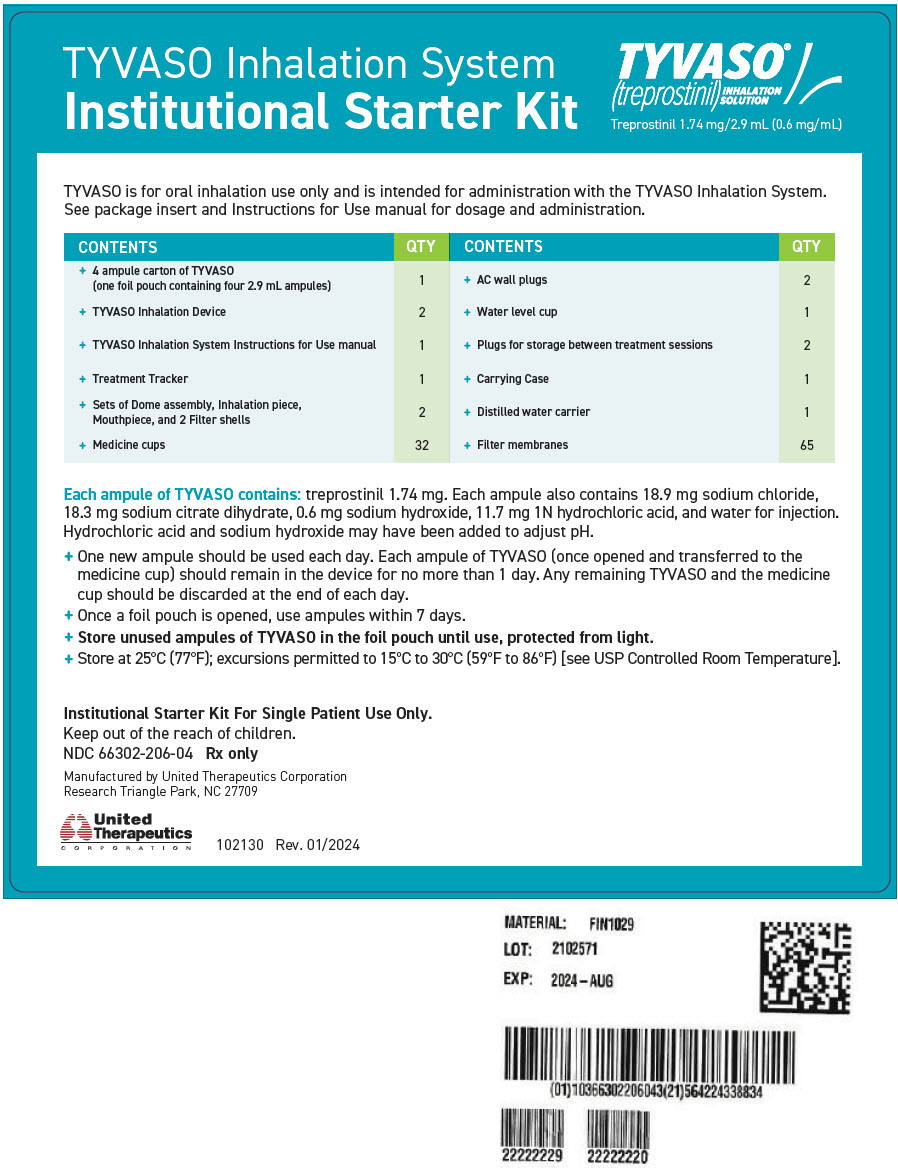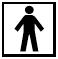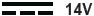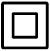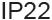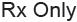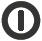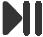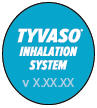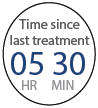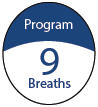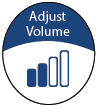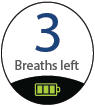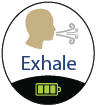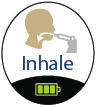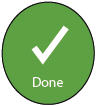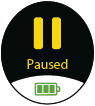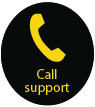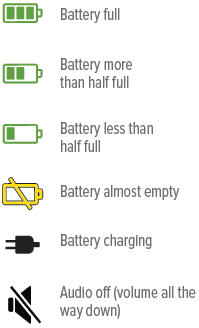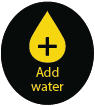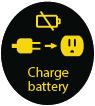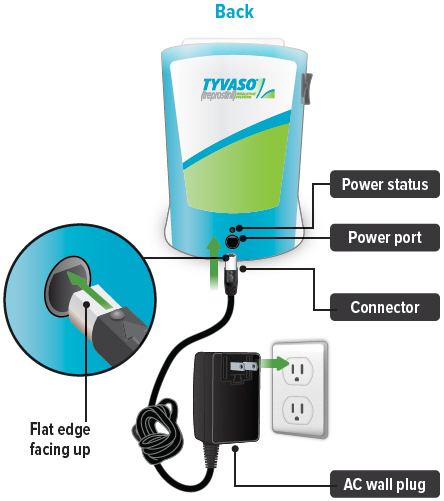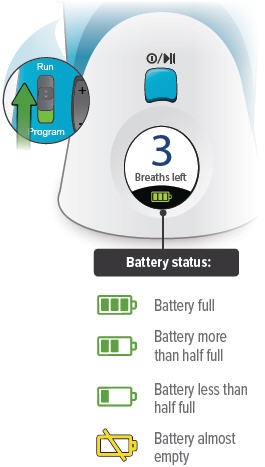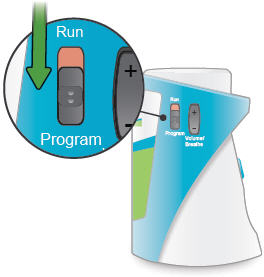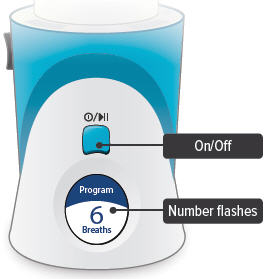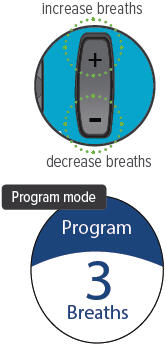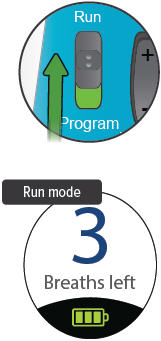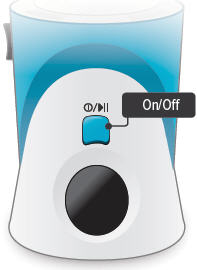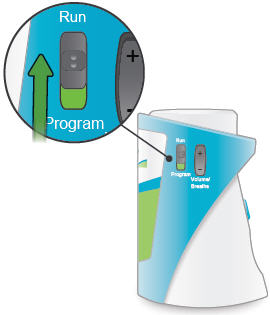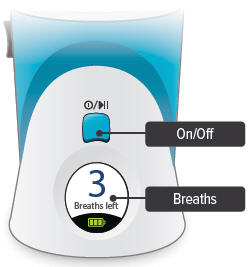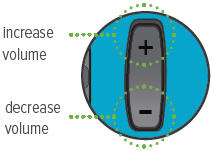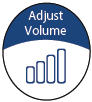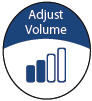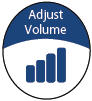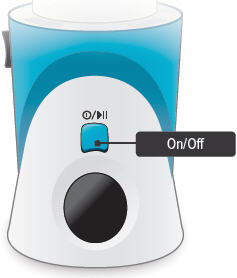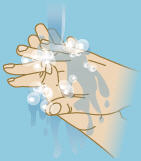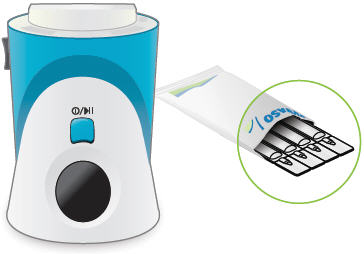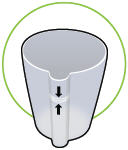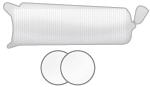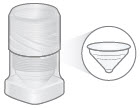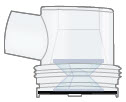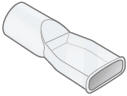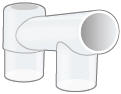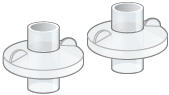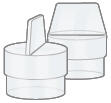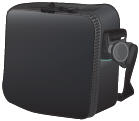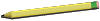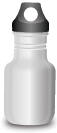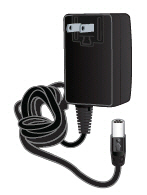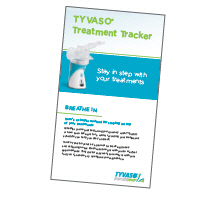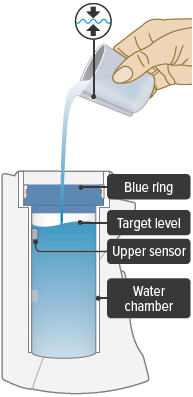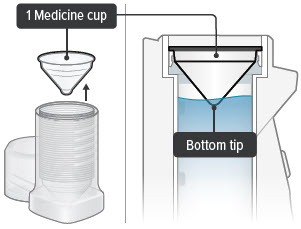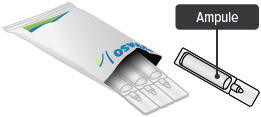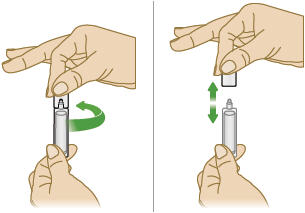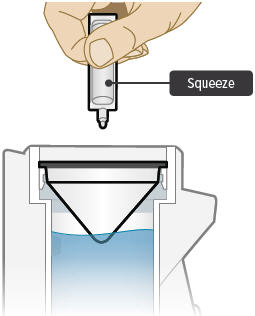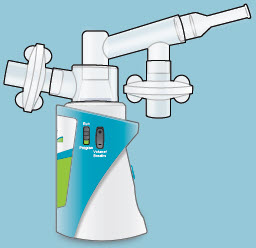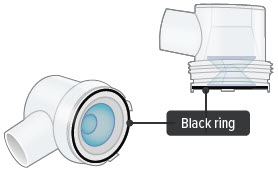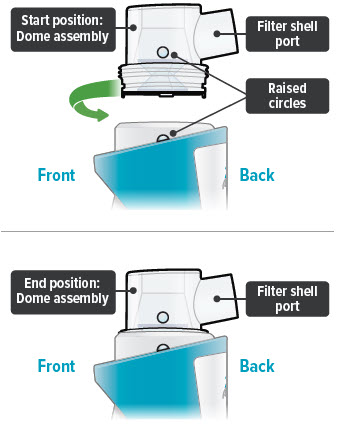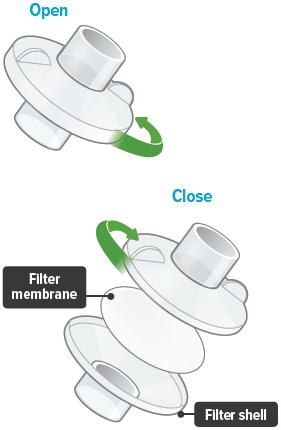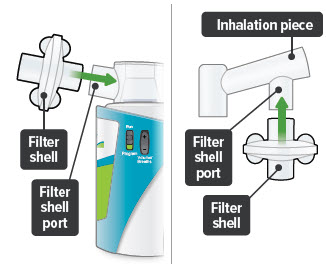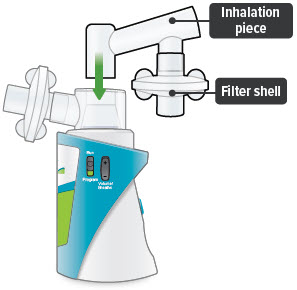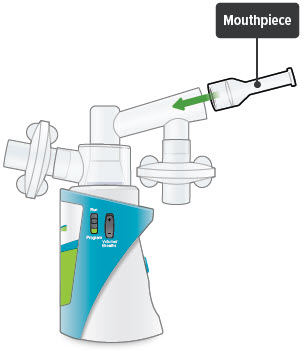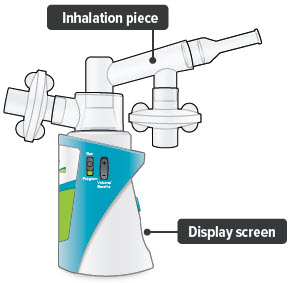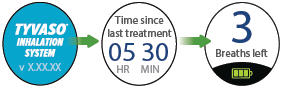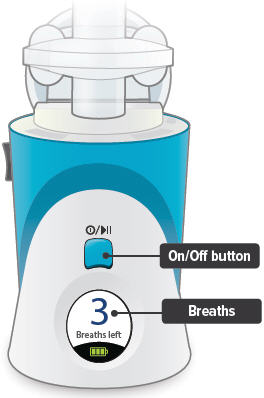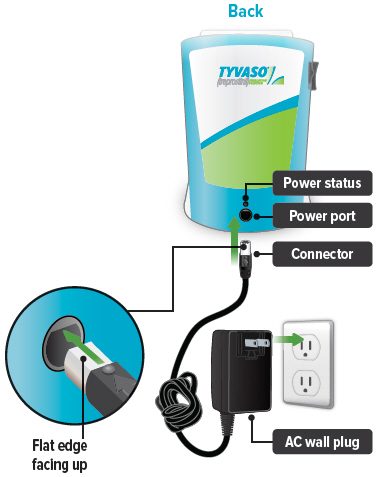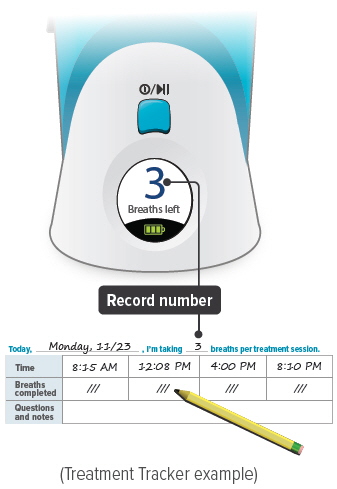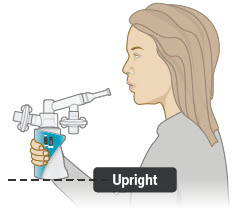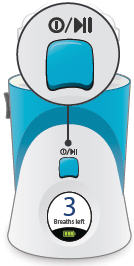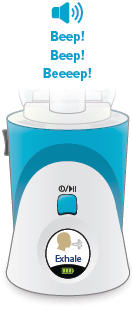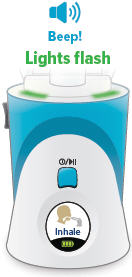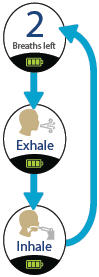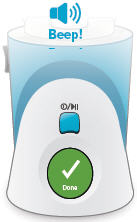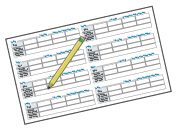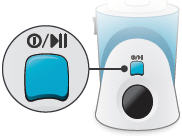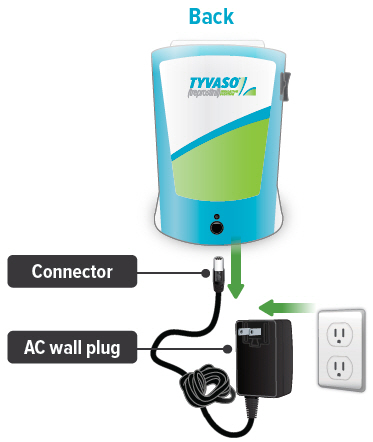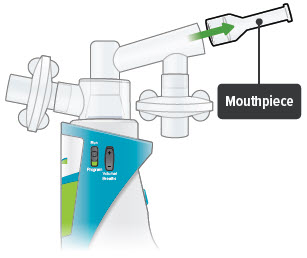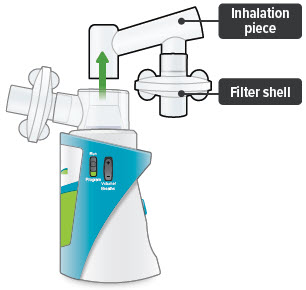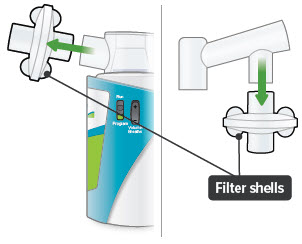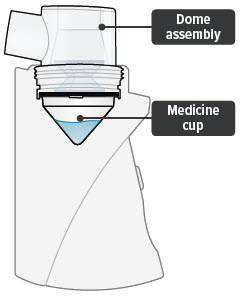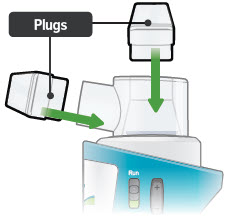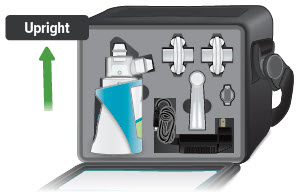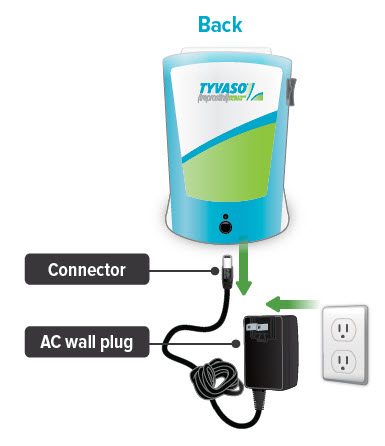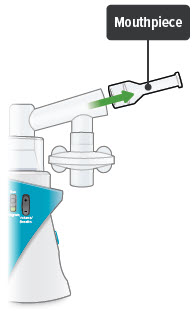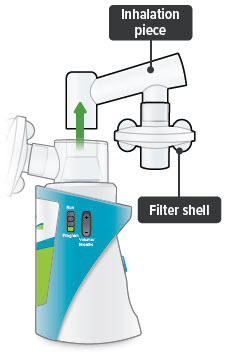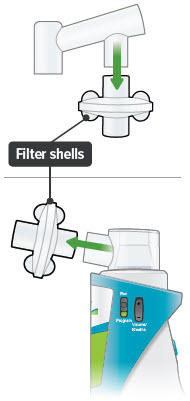 DRUG LABEL: TYVASO
NDC: 66302-206 | Form: INHALANT
Manufacturer: United Therapeutics Corporation
Category: prescription | Type: HUMAN PRESCRIPTION DRUG LABEL
Date: 20250808

ACTIVE INGREDIENTS: treprostinil 1.74 mg/2.9 mL
INACTIVE INGREDIENTS: sodium chloride 18.9 mg/2.9 mL; trisodium citrate dihydrate 18.3 mg/2.9 mL; sodium hydroxide 0.6 mg/2.9 mL; hydrochloric acid 11.7 mg/2.9 mL; water

HIGHLIGHTS OF PRESCRIBING INFORMATION

These highlights do not include all the information needed to use TYVASO safely and effectively. See full prescribing information for TYVASO.
TYVASO® (treprostinil) inhalation solution, for oral inhalation use
Initial U.S. Approval: 2002

RECENT MAJOR CHANGES

Warnings and Precautions (5.4) | 05/2022

1 INDICATIONS AND USAGE

Tyvaso is a prostacyclin mimetic indicated for the treatment of:

- Pulmonary arterial hypertension (PAH; WHO Group 1) to improve exercise ability. Studies establishing effectiveness predominately included patients with NYHA Functional Class III symptoms and etiologies of idiopathic or heritable PAH (56%) or PAH associated with connective tissue diseases (33%). (1.1)
- Pulmonary hypertension associated with interstitial lung disease (PH-ILD; WHO Group 3) to improve exercise ability. The study establishing effectiveness predominately included patients with etiologies of idiopathic interstitial pneumonia (IIP) (45%) inclusive of idiopathic pulmonary fibrosis (IPF), combined pulmonary fibrosis and emphysema (CPFE) (25%), and WHO Group 3 connective tissue disease (22%). (1.2)

2 DOSAGE AND ADMINISTRATION

- Use only with the Tyvaso Inhalation System. (2.1)
- Administer undiluted, as supplied. A single breath of Tyvaso delivers approximately 6 mcg of treprostinil. (2.1)
- Administer in 4 separate treatment sessions each day approximately 4 hours apart, during waking hours. (2.1)
- Initial dosage: 3 breaths (18 mcg) per treatment session. If 3 breaths are not tolerated, reduce to 1 or 2 breaths. (2.1)
- Dosage should be increased by an additional 3 breaths per treatment session at approximately 1- to 2-week intervals, if tolerated. (2.1)
- Titrate to target maintenance doses of 9 to 12 breaths per treatment session, 4 times daily. (2.1)

3 DOSAGE FORMS AND STRENGTHS

Sterile solution for oral inhalation: 2.9 mL ampule containing 1.74 mg treprostinil (0.6 mg per mL). (3)

4 CONTRAINDICATIONS

None. (4)

5 WARNINGS AND PRECAUTIONS

- Tyvaso may cause symptomatic hypotension. (5.1)
- Tyvaso inhibits platelet aggregation and increases the risk of bleeding. (5.2)
- Tyvaso dosage adjustments may be necessary if inhibitors or inducers of CYP2C8 are added or withdrawn. (5.3, 7.3)
- May cause bronchospasm: Patients with a history of hyperreactive airway disease may be more sensitive. (5.4)

6 ADVERSE REACTIONS

Most common adverse reactions (≥4%) are cough, headache, nausea, dizziness, flushing, throat irritation, pharyngolaryngeal pain, diarrhea, and syncope. (6)

To report SUSPECTED ADVERSE REACTIONS, contact United Therapeutics Corp. at 1-866-458-6479 or FDA at 1-800-FDA-1088 or www.fda.gov/medwatch.

FULL PRESCRIBING INFORMATION

1 INDICATIONS AND USAGE

1.1 Pulmonary Arterial Hypertension

Tyvaso is indicated for the treatment of pulmonary arterial hypertension (PAH; WHO Group 1) to improve exercise ability. Studies establishing effectiveness predominately included patients with NYHA Functional Class III symptoms and etiologies of idiopathic or heritable PAH (56%) or PAH associated with connective tissue diseases (33%).

The effects diminish over the minimum recommended dosing interval of 4 hours; treatment timing can be adjusted for planned activities.

While there are long-term data on use of treprostinil by other routes of administration, nearly all controlled clinical experience with inhaled treprostinil has been on a background of bosentan (an endothelin receptor antagonist) or sildenafil (a phosphodiesterase type 5 inhibitor). The controlled clinical experience was limited to 12 weeks in duration [see Clinical Studies (14)].

1.2 Pulmonary Hypertension Associated with ILD

Tyvaso is indicated for the treatment of pulmonary hypertension associated with interstitial lung disease (PH-ILD; WHO Group 3) to improve exercise ability. The study establishing effectiveness predominately included patients with etiologies of idiopathic interstitial pneumonia (IIP) (45%) inclusive of idiopathic pulmonary fibrosis (IPF), combined pulmonary fibrosis and emphysema (CPFE) (25%), and WHO Group 3 connective tissue disease (22%) [see Clinical Studies (14)].

2 DOSAGE AND ADMINISTRATION

2.1 Usual Dosage in Adults

Tyvaso is intended for oral inhalation using the Tyvaso Inhalation System, which consists of an ultrasonic, pulsed delivery device and its accessories.

Tyvaso is dosed in 4 separate, equally spaced treatment sessions per day, during waking hours. Each treatment session will take 2 to 3 minutes. The treatment sessions should be approximately 4 hours apart.

Initial Dosage:

Therapy should begin with 3 breaths of Tyvaso (18 mcg of treprostinil) per treatment session 4 times daily. If 3 breaths are not tolerated, reduce to 1 or 2 breaths and subsequently increase to 3 breaths, as tolerated.

Maintenance Dosage:

Dosage should be increased by an additional 3 breaths per treatment session, 4 times daily at approximately 1- to 2-week intervals. Studies establishing effectiveness in patients with PAH and PH-ILD have used target doses of 9 to 12 breaths per treatment session, 4 times daily. If adverse effects preclude titration to target dose, Tyvaso should be continued at the highest tolerated dose.

If a scheduled treatment session is missed or interrupted, therapy should be resumed as soon as possible at the usual dose.

2.2 Administration

Tyvaso must be used only with the Tyvaso Inhalation System. Patients should follow the instructions for use for operation of the Tyvaso Inhalation System and for daily cleaning of the device components after the last treatment session of the day. To avoid potential interruptions in drug delivery because of equipment malfunction, patients should have access to a back-up Tyvaso Inhalation System device.

Do not mix Tyvaso with other medications in the Tyvaso Inhalation System. Compatibility of Tyvaso with other medications has not been studied.

The Tyvaso Inhalation System should be prepared for use each day according to the instructions for use. One ampule of Tyvaso contains a sufficient volume of medication for all 4 treatment sessions in a single day. Prior to the first treatment session, the patient should twist the top off a single Tyvaso ampule and squeeze the entire contents into the medicine cup. Between each of the 4 daily treatment sessions, the device should be capped and stored upright with the remaining medication inside.

At the end of each day, the medicine cup and any remaining medication must be discarded. The device must be cleaned each day according to the instructions for use.

Avoid skin or eye contact with Tyvaso solution. Do not orally ingest the Tyvaso solution.

3 DOSAGE FORMS AND STRENGTHS

Sterile solution for oral inhalation: 2.9 mL ampule containing 1.74 mg of treprostinil (0.6 mg per mL).

4 CONTRAINDICATIONS

None.

5 WARNINGS AND PRECAUTIONS

5.1 Risk of Symptomatic Hypotension

Treprostinil is a pulmonary and systemic vasodilator. In patients with low systemic arterial pressure, treatment with Tyvaso may produce symptomatic hypotension.

5.2 Risk of Bleeding

Tyvaso inhibits platelet aggregation and increases the risk of bleeding.

5.3 Effect of Other Drugs on Treprostinil

Co-administration of a cytochrome P450 (CYP) 2C8 enzyme inhibitor (e.g., gemfibrozil) may increase exposure (both Cmax and AUC) to treprostinil. Co-administration of a CYP2C8 enzyme inducer (e.g., rifampin) may decrease exposure to treprostinil. Increased exposure is likely to increase adverse events associated with treprostinil administration, whereas decreased exposure is likely to reduce clinical effectiveness [see Drug Interactions (7.3) and Clinical Pharmacology (12.3)].

5.4 Bronchospasm

Like other inhaled prostaglandins, Tyvaso may cause acute bronchospasm. Patients with asthma or chronic obstructive pulmonary disease (COPD), or other bronchial hyperreactivity, are at increased risk for bronchospasm. Ensure that such patients are treated optimally for reactive airway disease prior to and during treatment with Tyvaso Inhalation Solution.

6 ADVERSE REACTIONS

The following potential adverse reactions are described in Warnings and Precautions (5):

- Decrease in systemic blood pressure [see Warnings and Precautions (5.1)].
- Bleeding [see Warnings and Precautions (5.2)].

6.1 Clinical Trials Experience

Because clinical trials are conducted under widely varying conditions, adverse reaction rates observed in the clinical trials of a drug cannot be directly compared to rates in the clinical trials of another drug and may not reflect the rates observed in practice.

Pulmonary Arterial Hypertension

In a 12-week, placebo-controlled study (TRIUMPH I) of 235 patients with PAH (WHO Group 1 and nearly all NYHA Functional Class III), the most commonly reported adverse reactions on Tyvaso included cough and throat irritation, headache, gastrointestinal effects, muscle, jaw or bone pain, dizziness, flushing, and syncope. Table 1 lists the adverse reactions that occurred at a rate of at least 4% and were more frequent in patients treated with Tyvaso than with placebo.

Table 1: Adverse Events in ≥4% of PAH Patients Receiving Tyvaso and More Frequent [More than 3% greater than placebo] than Placebo in TRIUMPH I
Adverse Event | Treatment n (%)
Adverse Event | Tyvaso n=115 | Placebo n=120
Cough | 62 (54) | 35 (29)
Headache | 47 (41) | 27 (23)
Throat Irritation / Pharyngolaryngeal Pain | 29 (25) | 17 (14)
Nausea | 22 (19) | 13 (11)
Flushing | 17 (15) | 1 (<1)
Syncope | 7 (6) | 1 (<1)

The safety of Tyvaso was also studied in a long-term, open-label extension study in which 206 patients were dosed for a mean duration of 2.3 years, with a maximum exposure of 5.4 years. Eighty-nine percent (89%) of patients achieved the target dose of 9 breaths, 4 times daily. Forty-two percent (42%) achieved a dose of 12 breaths, 4 times daily. The adverse events during this chronic dosing study were qualitatively similar to those observed in the 12-week placebo-controlled trial.

In a prospective, observational study comparing patients taking Tyvaso (958 patient-years of exposure) and a control group (treatment with other approved therapies for PAH; 1094 patient-years), Tyvaso was associated with a higher rate of cough (16.2 vs. 10.9 per 100 patient-years), throat irritation (4.5 vs. 1.2 per 100 pt-years), nasal discomfort (2.6 vs. 1.3 per 100 pt-years), and hemoptysis (2.5 vs. 1.3 per 100 pt-years) compared to the control group.

Pulmonary Hypertension Associated with ILD

In a 16-week, placebo-controlled study (INCREASE) of 326 patients with PH-ILD (WHO Group 3), adverse reactions were similar to the experience in studies of PAH.

6.2 Post-Marketing Experience

The adverse reaction of angioedema has been identified during the post-approval use of Tyvaso. Because this reaction is reported voluntarily from a population of uncertain size, it is not always possible to reliably estimate the frequency or establish a causal relationship to drug exposure.

7 DRUG INTERACTIONS

7.1 Bosentan

In a human pharmacokinetic study conducted with bosentan (250 mg/day) and an oral formulation of treprostinil (treprostinil diolamine), no pharmacokinetic interactions between treprostinil and bosentan were observed.

7.2 Sildenafil

In a human pharmacokinetic study conducted with sildenafil (60 mg/day) and an oral formulation of treprostinil (treprostinil diolamine), no pharmacokinetic interactions between treprostinil and sildenafil were observed.

7.3 Effect of Cytochrome P450 Inhibitors and Inducers

In vitro studies of human hepatic microsomes showed that treprostinil does not inhibit cytochrome P450 (CYP) isoenzymes CYP1A2, CYP2A6, CYP2C8, CYP2C9, CYP2C19, CYP2D6, CYP2E1, and CYP3A. Additionally, treprostinil does not induce cytochrome P450 isoenzymes CYP1A2, CYP2B6, CYP2C9, CYP2C19, and CYP3A.

Human pharmacokinetic studies with an oral formulation of treprostinil (treprostinil diolamine) indicated that co-administration of the cytochrome P450 (CYP) 2C8 enzyme inhibitor, gemfibrozil, increases exposure (both Cmax and AUC) to treprostinil. Co-administration of the CYP2C8 enzyme inducer, rifampin, decreases exposure to treprostinil. It is unclear if the safety and efficacy of treprostinil by the inhalation route are altered by inhibitors or inducers of CYP2C8 [see Warnings and Precautions (5.3)].

7.4 Effect of Other Drugs on Treprostinil

Drug interaction studies have been carried out with treprostinil (oral or subcutaneous) co-administered with acetaminophen (4 g/day), warfarin (25 mg/day), and fluconazole (200 mg/day), respectively, in healthy volunteers. These studies did not show a clinically significant effect on the pharmacokinetics of treprostinil. Treprostinil does not affect the pharmacokinetics or pharmacodynamics of warfarin. The pharmacokinetics of R- and S- warfarin and the international normalized ratio (INR) in healthy subjects given a single 25 mg dose of warfarin were unaffected by continuous subcutaneous infusion of treprostinil at an infusion rate of 10 ng/kg/min.

8 USE IN SPECIFIC POPULATIONS

8.1 Pregnancy

Risk Summary

Limited case reports of treprostinil use in pregnant women are insufficient to inform a drug-associated risk of adverse developmental outcomes. However, there are risks to the mother and the fetus associated with pulmonary arterial hypertension (see Clinical Considerations). In animal studies, no adverse reproductive and developmental effects were seen for treprostinil at ≥9 and ≥145 times the human exposure when based on Cmax and AUC, respectively, following a single treprostinil dose of 54 mcg.

The estimated background risk of major birth defects and miscarriage for the indicated populations is unknown. All pregnancies have a background risk of birth defect, loss, or other adverse outcomes. In the U.S. general population, the estimated background risk of major birth defects and miscarriage in clinically recognized pregnancies is 2 to 4% and 15 to 20%, respectively.

Clinical Considerations

Disease-associated maternal and embryo-fetal risk

Pulmonary arterial hypertension is associated with an increased risk of maternal and fetal mortality.

Data

Animal reproduction studies have been conducted with treprostinil via continuous subcutaneous administration and with treprostinil diolamine administered orally. In studies with orally administered treprostinil diolamine, no adverse effect doses for fetal viability/growth, fetal development (teratogenicity), and postnatal development were determined in rats. In pregnant rats, no evidence of harm to the fetus was observed following oral administration of treprostinil diolamine at the highest dose tested (20 mg/kg/day), which represents about 154 and 1479 times the human exposure, when based on Cmax and AUC, respectively, following a single Tyvaso dose of 54 mcg. In pregnant rabbits, external fetal and soft tissue malformations and fetal skeletal malformation occurred. The dose at which no adverse effects were seen (0.5 mg/kg/day) represents about 9 and 145 times the human exposure, when based on Cmax and AUC, respectively, following a single Tyvaso dose of 54 mcg. No treprostinil treatment-related effects on labor and delivery were seen in animal studies. Animal reproduction studies are not always predictive of human response.

8.2 Lactation

Risk Summary

There are no data on the presence of treprostinil in human milk, the effects on the breastfed infant, or the effects on milk production.

8.4 Pediatric Use

Safety and effectiveness in pediatric patients have not been established. Clinical studies of Tyvaso did not include patients younger than 18 years to determine whether they respond differently from older patients.

8.5 Geriatric Use

Across clinical studies used to establish the effectiveness of Tyvaso in patients with PAH and PH-ILD, 268 (47.8%) patients aged 65 years and over were enrolled. The treatment effects and safety profile observed in geriatric patients were similar to younger patients. In general, dose selection for an elderly patient should be cautious, reflecting the greater frequency of hepatic, renal, or cardiac dysfunction, and of concomitant diseases or other drug therapy.

8.6 Patients with Hepatic Insufficiency

Plasma clearance of treprostinil, delivered subcutaneously, was reduced up to 80% in subjects with mild-to-moderate hepatic insufficiency. Uptitrate slowly when treating patients with hepatic insufficiency because of the risk of an increase in systemic exposure which may lead to an increase in dose-dependent adverse effects. Treprostinil has not been studied in patients with severe hepatic insufficiency [see Clinical Pharmacology (12.3)].

8.7 Patients with Renal Impairment

No dose adjustments are required in patients with renal impairment. Treprostinil is not cleared by dialysis [see Clinical Pharmacology (12.3)].

10 OVERDOSAGE

In general, symptoms of overdose with Tyvaso include flushing, headache, hypotension, nausea, vomiting, and diarrhea. Provide general supportive care until the symptoms of overdose have resolved.

11 DESCRIPTION

Tyvaso is a sterile formulation of treprostinil, a prostacyclin mimetic, intended for administration by oral inhalation using the Tyvaso Inhalation System. Tyvaso is supplied in 2.9 mL low density polyethylene (LDPE) ampules, containing 1.74 mg treprostinil (0.6 mg/mL). Each ampule also contains 18.9 mg sodium chloride, 18.3 mg sodium citrate dihydrate, 0.58 mg sodium hydroxide, 11.7 mg 1 N hydrochloric acid, and water for injection. Sodium hydroxide and hydrochloric acid may be added to adjust pH between 6.0 and 7.2.

Treprostinil is (1R,2R,3aS,9aS)-[[2,3,3a,4,9,9a-hexahydro-2-hydroxy-1-[(3S)-3-hydroxyoctyl]-1H-benz[f]inden-5-yl]oxy]acetic acid. Treprostinil has a molecular weight of 390.52 and a molecular formula of C23H34O5.

The structural formula of treprostinil is:

12 CLINICAL PHARMACOLOGY

12.1 Mechanism of Action

Treprostinil is a prostacyclin analogue. The major pharmacologic actions of treprostinil are direct vasodilation of pulmonary and systemic arterial vascular beds and inhibition of platelet aggregation.

12.2 Pharmacodynamics

In a clinical trial of 240 healthy volunteers, single doses of Tyvaso 54 mcg (the target maintenance dose per session) and 84 mcg (supratherapeutic inhalation dose) prolonged the corrected QTc interval by approximately 10 ms. The QTc effect dissipated rapidly as the concentration of treprostinil decreased.

12.3 Pharmacokinetics

Pharmacokinetic information for single doses of inhaled treprostinil was obtained in healthy volunteers in 3 separate studies. Treprostinil systemic exposure (AUC and Cmax) post-inhalation was shown to be proportional to the doses administered (18 mcg to 90 mcg).

Absorption

In a 3-period crossover study, the bioavailability of 2 single doses of Tyvaso (18 mcg and 36 mcg) was compared with that of intravenous treprostinil in 18 healthy volunteers. Mean estimates of the absolute systemic bioavailability of treprostinil after inhalation were approximately 64% (18 mcg) and 72% (36 mcg).

Treprostinil plasma exposure data were obtained from 2 studies at the target maintenance dose, 54 mcg. The mean Cmax at the target dose was 0.91 and 1.32 ng/mL with corresponding mean Tmax of 0.25 and 0.12 hr, respectively. The mean AUC for the 54-mcg dose was 0.81 and 0.97 hr∙ng/mL, respectively.

Distribution

Following parenteral infusion, the apparent steady state volume of distribution (Vss) of treprostinil is approximately 14 L/70 kg ideal body weight.

In vitro treprostinil is 91% bound to human plasma proteins over the 330 to 10,000 mcg/L concentration range.

Metabolism and Excretion

Of subcutaneously administered treprostinil, only 4% is excreted unchanged in urine. Treprostinil is substantially metabolized by the liver, primarily by CYP2C8. Metabolites are excreted in urine (79%) and feces (13%) over 10 days. Five apparently inactive metabolites were detected in the urine, each accounting for 10 to 15% of the dose administered. Four of the metabolites are products of oxidation of the 3-hydroxyloctyl side chain and 1 is a glucuroconjugated derivative (treprostinil glucuronide).

The elimination of treprostinil (following subcutaneous administration of treprostinil) is biphasic, with a terminal elimination half-life of approximately 4 hours using a 2-compartment model.

Specific Populations

Hepatic Insufficiency

Plasma clearance of treprostinil, delivered subcutaneously, was reduced up to 80% in subjects presenting with mild-to-moderate hepatic insufficiency. Treprostinil has not been studied in patients with severe hepatic insufficiency [see Use in Specific Populations (8.6)].

Renal Impairment

In patients with severe renal impairment requiring dialysis (n=8), administration of a single 1 mg dose of orally administered treprostinil pre- and post-dialysis resulted in AUC0-inf that was not significantly altered compared to healthy subjects [see Use in Specific Populations (8.7)].

13 NONCLINICAL TOXICOLOGY

13.1 Carcinogenesis, Mutagenesis, Impairment of Fertility

A 2-year rat carcinogenicity study was performed with treprostinil inhalation at target doses of 5.26, 10.6, and 34.1 mcg/kg/day. There was no evidence for carcinogenic potential associated with treprostinil inhalation in rats at systemic exposure levels up to 35 times the clinical exposure at the target maintenance dose of 54 mcg. In vitro and in vivo genetic toxicology studies did not demonstrate any mutagenic or clastogenic effects of treprostinil. Treprostinil sodium did not affect fertility or mating performance of male or female rats given continuous subcutaneous infusions at rates of up to 450 ng treprostinil/kg/min. In this study, males were dosed from 10 weeks prior to mating and through the 2-week mating period. Females were dosed from 2 weeks prior to mating until gestational day 6.

Oral administration of treprostinil diolamine to Tg.rasH2 mice at 0, 5, 10, and 20 mg/kg/day in males and 0, 3, 7.5, and 15 mg/kg/day in females daily for 26 weeks did not significantly increase the incidence of tumors.

Treprostinil diolamine was tested in vivo in a rat micronucleus assay and did not induce an increased incidence of micronucleated polychromatic erythrocytes.

13.2 Animal Toxicology and/or Pharmacology

In a 2-year rat study with treprostinil inhalation at target doses of 5.26, 10.6, and 34.1 mcg/kg/day, there were more deaths (11) in the mid- and high-dose treprostinil groups during the first 9 weeks of the study, compared to 1 in control groups. At the high-dose level, males showed a higher incidence of inflammation in teeth and preputial gland, and females showed higher incidences of inflammation and urothelial hyperplasia in the urinary bladder. The exposures in rats at mid- and high-dose levels were about 15 and 35 times, respectively, the clinical exposure at the target maintenance dose of 54 mcg.

14 CLINICAL STUDIES

14.1 Pulmonary Arterial Hypertension (WHO Group 1)

TRIUMPH I, was a 12-week, randomized, double-blind, placebo-controlled, multicenter study of patients with PAH. The study population included 235 clinically stable subjects with PAH (WHO Group 1), nearly all with NYHA Class III (98%) symptoms who were receiving either bosentan (an endothelin receptor antagonist) or sildenafil (a phosphodiesterase-5 inhibitor) for at least 3 months prior to study initiation. Concomitant therapy also could have included anticoagulants, other vasodilators (e.g., calcium channel blockers), diuretics, oxygen, and digitalis, but not a prostacyclin. These patients were administered either placebo or Tyvaso in 4 daily treatment sessions with a target dose of 9 breaths (54 mcg) per session over the course of the 12-week study. Patients were predominately female (82%), had the origin of PAH as idiopathic/heritable (56%), secondary to connective tissue diseases (33%) or secondary to HIV or previous use of anorexigens (12%); bosentan was the concomitant oral medication in 70% of those enrolled, sildenafil in 30%.

The primary efficacy endpoint of the trial was the change in 6-Minute Walk Distance (6MWD) relative to baseline at 12 weeks. 6MWD was measured at peak exposure (between 10 and 60 minutes after dosing), and 3 to 5 hours after bosentan or 0.5 to 2 hours after sildenafil. Patients receiving Tyvaso had a placebo-corrected median change from baseline in peak 6MWD of 20 meters at Week 12 (p<0.001). The distribution of these 6MWD changes from baseline at Week 12 were plotted across the range of observed values (Figure 1). 6MWD measured at trough exposure (defined as measurement of 6MWD at least 4 hours after dosing) improved by 14 meters. There were no placebo-controlled 6MWD assessments made after 12 weeks.

Figure 1: Distributions of 6MWD Changes from Baseline at Week 12 During Peak Plasma Concentration of Tyvaso

The placebo-corrected median treatment effect on 6MWD was estimated (using the Hodges-Lehmann estimator) within various subpopulations defined by age quartile, gender, geographic region of the study site, disease etiology, baseline 6MWD quartile, and type of background therapy (Figure 2).

Figure 2: Placebo-Corrected Median Treatment Effect (Hodges-Lehmann Estimate with 95% CI) on 6MWD Change from Baseline at Week 12 During Peak Plasma Concentration of Tyvaso for Various Subgroups

14.2 Long-term Treatment of PAH

In long-term follow-up of patients who were treated with Tyvaso in the pivotal study and the open-label extension (N=206), Kaplan-Meier estimates of survival at 1, 2, and 3 years were 97%, 91%, and 82%, respectively. These uncontrolled observations do not allow comparison with a control group not given Tyvaso and cannot be used to determine the long-term effect of Tyvaso on mortality.

14.3 Pulmonary Hypertension Associated with ILD (WHO Group 3)

INCREASE was a 16-week, randomized, double-blind, placebo-controlled, multicenter study that enrolled 326 patients with PH-ILD. Enrolled study patients predominately had etiologies of idiopathic interstitial pneumonia (45%) inclusive of idiopathic pulmonary fibrosis, combined pulmonary fibrosis and emphysema (25%), and WHO Group 3 connective tissue disease (22%). The mean baseline 6MWD was 260 meters.

Patients in the INCREASE study were randomized (1:1) to either placebo or Tyvaso in 4 daily treatment sessions with a target dose of 9 breaths (54 mcg) per session and a maximum dose of 12 breaths (72 mcg) per session over the course of the 16-week study. Approximately 75% of patients randomized to Tyvaso titrated up to a dose of 9 breaths, 4 times daily or greater, with 48% of patients randomized to Tyvaso reaching a dose of 12 breaths, 4 times daily during the study.

The primary efficacy endpoint was the change in 6MWD measured at peak exposure (between 10 and 60 minutes after dosing) from baseline to Week 16. Patients receiving Tyvaso had a placebo-corrected median change from baseline in peak 6MWD of 21 meters at Week 16 (p=0.004) using Hodges-Lehmann estimate (Figure 3).

Figure 3: Hodges-Lehmann Estimate of Treatment Effect by Visit for 6MWD at Peak Exposure (PH-ILD)

The treatment effect on 6MWD at Week 16 was consistent for various subgroups, including etiology of PH-ILD, disease severity, age, sex, baseline hemodynamics, and dose (Figure 4).

Figure 4: Forest Plot on Subgroup Analyses of Peak 6MWD (Meter) at Week 16 (PH-ILD)

Time to clinical worsening in the INCREASE study was defined as the time of randomization until 1 of the following criteria were met: hospitalization due to a cardiopulmonary indication, decrease in 6MWD >15% from baseline directly related to PH-ILD at 2 consecutive visits and at least 24 hours apart, death (all causes), or lung transplantation. Treatment with Tyvaso in patients with PH-ILD resulted in numerically fewer hospitalizations. The numbers of reported deaths were the same for both treatment groups (Table 2). Overall, treatment with Tyvaso demonstrated a statistically significant increase in the time to first clinical worsening event (log-rank test p=0.041; Figure 5), and a 39% overall reduction in the risk of a clinical worsening event (HR=0.61 [95% CI; 0.40, 0.92]; Figure 5).

Table 2: Clinical Worsening Events (PH-ILD)
 |  | Tyvaso n=163 n (%) | Placebo n=163 n (%) | HR (95% CI)
Clinical worsening |  | 37 (22.7%) | 54 (33.1%) | 0.61 (0.40, 0.92)
First contributing event | Hospitalization due to a cardiopulmonary indication | 18 (11.0%) | 24 (14.7%)
First contributing event | Decrease in 6MWD >15% from baseline directly related to PH-ILD | 13 (8.0%) | 26 (16.0%)
First contributing event | Death (all causes) | 4 (2.5%) | 4 (2.5%)
First contributing event | Lung transplantation | 2 (1.2%) | 0
First of each event | Hospitalization due to a cardiopulmonary indication | 21 (12.9%) | 30 (18.4%)
First of each event | Decrease in 6MWD >15% from baseline directly related to PH-ILD | 16 (9.8%) | 31 (19.0%)
First of each event | Death (all causes) | 8 (4.9%) | 10 (6.1%)
First of each event | Lung transplantation | 2 (1.2%) | 1 (0.6%)

Figure 5: Kaplan-Meier Plot of Time to Clinical Worsening Events (PH-ILD)

16 HOW SUPPLIED/STORAGE AND HANDLING

Tyvaso (treprostinil) inhalation solution is supplied in 2.9 mL clear LDPE ampules packaged as 4 ampules in a foil pouch. Tyvaso is a clear colorless to slightly yellow solution containing 1.74 mg treprostinil per ampule at a concentration of 0.6 mg/mL.

STORAGE AND HANDLING

Ampules of Tyvaso are stable until the date indicated when stored in the unopened foil pouch at 20-25°C (68-77°F) with excursions permitted to 15-30°C (59-86°F) [see USP Controlled Room Temperature]. Once the foil pack is opened, ampules should be used within 7 days. Because Tyvaso is light-sensitive, unopened ampules should be stored in the foil pouch.

One ampule of Tyvaso should be used each day in the Tyvaso Inhalation System. After a Tyvaso ampule is opened and transferred to the medicine cup, the solution should remain in the device for no more than 1 day (24 hours). Any remaining solution should be discarded at the end of the day.

Tyvaso Inhalation System Starter Kit containing a 28-ampule carton of Tyvaso (7 foil pouches each containing four 2.9 mL ampules; each ampule contains 1.74 mg treprostinil [0.6 mg per mL]) and the Tyvaso Inhalation System. (NDC 66302-206-01)

Tyvaso Inhalation System Refill Kit containing a 28-ampule carton of Tyvaso (7 foil pouches each containing four 2.9 mL ampules; each ampule contains 1.74 mg treprostinil [0.6 mg per mL]) and accessories. (NDC 66302-206-02)

Tyvaso 4 Pack Carton with 1 foil pouch containing four 2.9 mL ampules. Each ampule contains 1.74 mg treprostinil (0.6 mg per mL). (NDC 66302-206-03)

Tyvaso Inhalation System Institutional Starter Kit containing a 4-ampule carton of Tyvaso (1 foil pouch containing four 2.9 mL ampules; each ampule contains 1.74 mg treprostinil [0.6 mg per mL]) and the Tyvaso Inhalation System. (NDC 66302-206-04)

17 PATIENT COUNSELING INFORMATION

Advise the patient to read the FDA-approved patient labeling (Instructions for Use).

Train patients in the administration process for Tyvaso, including dosing, Tyvaso Inhalation System set up, operation, cleaning, and maintenance, according to the instructions for use [see Dosage and Administration (2.1, 2.2)].

To avoid potential interruptions in drug delivery because of equipment malfunction, patients should have access to a back-up Tyvaso Inhalation System device [see Dosage and Administration (2.2)].

In the event that a scheduled treatment session is missed or interrupted, resume therapy as soon as possible [see Dosage and Administration (2.1)].

If Tyvaso comes in contact with the skin or eyes, instruct patients to rinse immediately with water [see Dosage and Administration (2.2)].

©Copyright 2022 United Therapeutics Corp. All rights reserved.

Tyvaso manufactured for:

United Therapeutics Corp.
Research Triangle Park, NC 27709

INSTRUCTIONS FOR USE

TYVASO®
INHALATION SYSTEM

Instructions for Use Manual

TYVASO®
(treprostinil)
INHALATION
SOLUTION

Contents

Overview of your TYVASO Inhalation System | 4
Introduction | 6
Safety and general instructions | 8
Buttons, indicators, and markings | 10
Inhalation device display screens | 16
Programming your TYVASO Inhalation System before use | 18
Charging device before use | 20
Setting your prescribed dose | 22
Adjusting device's audio volume | 24
Preparing and using your TYVASO Inhalation System for daily treatments | 26
Prepare a proper environment | 28
Gather supplies | 29
Fill water chamber and medicine cup | 32
Assemble inhalation device | 35
Power on inhalation device | 40
Inhale your medicine | 42
Cleaning and Storing your TYVASO Inhalation System | 46
Storing between sessions during the day | 48
End of day cleaning | 52
Recharging the battery | 57
Weekly cleaning | 59
Monthly Refill Kit | 60
Replacing your devices | 61
Help / More information about your TYVASO Inhalation System | 62
Troubleshooting | 64
Specifications | 76
Electromagnetic compatibility (EMC) | 79
Glossary | 87
Warranty information | 90

Overview of your TYVASO Inhalation System

Section overview

This section introduces you to your TYVASO Inhalation System and provides important safety information about using your system.

What you will need:

▶ A clean place to review these instructions

▶ TYVASO Inhalation System to refer to while reading instructions

What is covered in this section:
A: Introduction | 6
B: Safety and general instructions | 8
C: Buttons, indicators, and markings | 10
D: Inhalation device display screens | 16

Important:

Do not start treatment with TYVASO until you have been trained to use the TYVASO Inhalation System. Make sure you understand all of the directions. Always ask your doctor or specialty pharmacy provider if you have any questions or are unsure of anything you are taught.

A: Introduction

Your doctor has prescribed TYVASO® (treprostinil) Inhalation Solution. Please see the accompanying Patient Information for important safety information on TYVASO.

TYVASO is a prescription medicine used in adults to treat pulmonary arterial hypertension (PAH; WHO Group 1) and pulmonary hypertension associated with interstitial lung disease (PH-ILD; WHO Group 3), which are diseases causing high blood pressure in the arteries of your lungs. TYVASO can improve exercise ability. The effects decrease over 4 hours; treatment timing can be adjusted for planned activities.

TYVASO is breathed in (inhaled) using the TYVASO Inhalation System, which consists of the inhalation device and its accessories.

This Instructions for Use manual for the TYVASO Inhalation System provides important safety information. It is important that you read these instructions and the TYVASO Patient Information before setting up and using the TYVASO Inhalation System. If you have any questions, talk to your doctor or specialty pharmacy provider.

Before beginning treatment with TYVASO, you will receive either a Patient Starter Kit containing a 28-day supply of TYVASO or an Institutional Starter Kit containing a 4-day supply of medication.

Both kits include 2 complete inhalation devices (all accessories and supplies included). When you refill your prescription for TYVASO each month, you will receive a Refill Kit that contains a 28-day supply of TYVASO and new accessories. You will receive replacement devices every 2 years from your date of receipt of the TYVASO Inhalation System.

CAUTION: Federal law restricts this device to sale by or on the order of a physician, or other licensed practitioner.

Important:

- Keep this Instructions for Use manual in a safe place where you can easily get to it for reference. For example, store the booklet in the TYVASO Inhalation System carrying case, along with your other supplies.
- TYVASO Inhalation System is intended solely for the delivery of TYVASO (treprostinil) Inhalation Solution. TYVASO is for administration only with the TYVASO Inhalation System.

B: Safety and general instructions

The TYVASO Inhalation System should be handled carefully. Take the following precautions and follow all instructions in this document to avoid injury and ensure proper use:

Delivering treatments:

- Read the instructions carefully and completely to prevent damage to your TYVASO Inhalation System and help you get the best results.
- This device should only be used on the order of your doctor or licensed healthcare practitioner.
- Conduct only the number of treatment sessions and inhalations you have been prescribed.
- Ensure the breath counter is correctly programmed prior to beginning a treatment (see page 22).
- Turn off the device when not in use.
- Do not use the device with an anesthetic breathing system or ventilator breathing system.
- Use only the supplies provided in the Starter Kit and Monthly Refill Kit for correct device function.

Handling the device:

- Do not peel or remove the labels from the device.
- Do not drop the device.
- The device does not include internal, replaceable parts. Do not attempt to open the device, modify the device, or remove device labeling.

Your environment:

- Do not leave the device alone with a small child.
- Do not immerse the device in water or other liquids, or place in dishwasher.
- Do not place any system components in a microwave, conventional oven, or dishwasher.
- Do not use the device near flammable liquids and materials or heated surfaces.
- Do not place the device or use the device in the presence of strong electric or magnetic fields (e.g., microwave oven, magnetic imaging equipment).
- Wireless communications equipment (e.g., cell phone) can affect operation of the device and should be kept at least a distance of 3.3 meters (about 11 feet) away while using the device.
- If the device performance is affected by exposure to any conditions listed here, see the Troubleshooting section, or contact your healthcare provider or specialty pharmacy provider.

C: Buttons, indicators, and markings

Inhalation device

Inhalation indicator lights

Lights on top of device flash green when you should inhale.

On/Off, Start/Pause (blue) button

Press and hold to power device on or off. Once device is on, press and immediately release (do not hold down) to start or pause treatment.

Device Display

Provides instructions and device information.

Run / Program switch

Slide up to Run mode when you are ready to deliver your dose. Slide down to Program mode to program the number of breaths for your dose.

Volume / Breaths toggle button

When set to Run mode, push + to increase beeping volume, or push - to decrease beeping volume.

When set to Program mode, push + to increase the number of breaths, or push - to decrease the number of breaths required for each dose.

Power status light

Lights green when power is connected and battery is charging.

Power port

Port for plugging into a power source using the AC wall plug.

Additional device markings

Manufacturer. Indicates the medical device manufacturer.
(Symbol 5.1.1 of ANSI/AAMI/ISO 15223-1: 2012 Medical devices - symbols to be used with medical devices labels, labeling, and information to be supplied - part 1: general requirements)

Equipment should not be disposed of in the trash.
(Figure 1 of BS EN 50419:2006 - Marking of Electrical and Electronic Equipment in accordance with Article 11(2) of Directive 2002/96/EC (WEEE))

Catalogue number. Indicates the manufacturer's catalogue number so that the medical device can be identified. (Symbol 5.1.6 of ANSI/AAMI/ISO 15223-1: 2012 Medical devices - symbols to be used with medical devices labels, labeling, and information to be supplied - part 1: general requirements)

Serial number. Indicates the manufacturer's serial number so that a specific medical device can be identified. (Symbol 5.1.7 of ANSI/AAMI/ISO 15223-1: 2012 Medical devices - symbols to be used with medical devices labels, labeling, and information to be supplied - part 1: general requirements)

Consult instructions for use. Please read the accompanying instructions and labels for important information regarding the TYVASO Inhalation System. (Symbol 5.4.3 of ANSI/AAMI/ISO 15223-1: 2012 Medical devices - symbols to be used with medical devices labels, labeling, and information to be supplied - part 1: general requirements)

The TYVASO Inhalation System has a Type BF Applied part. Type BF Applied parts comply with specific requirements to provide protection against shock and are not suitable for direct cardiac applications.
(Symbol 5333 of IEC 60417 Database Snapshot - Graphical symbols for use on equipment)

The TYVASO Inhalation System requires a 14V DC power supply. Use only the power supply intended for the TYVASO Inhalation System.
(Direct Current, Symbol 5031 of IEC 60417 Database Snapshot - Graphical symbols for use on equipment)

The TYVASO Inhalation System complies with the requirements of Protection Class II. Class II equipment provides additional precautions, over and above basic insulation, to provide protection against electric shock. (Class II equipment, Symbol 5172 of IEC 60417 Database Snapshot - Graphical symbols for use on equipment)

The TYVASO Inhalation Device provides level 2 solid particle protection and level 2 liquid ingress protection per IEC 60529 specifications.

The TYVASO Inhalation System should only be used on the order of your doctor or licensed healthcare provider. (Symbol statement as provided under 21 CFR 801.109(b)(1))

Power stand by. Indicates the control for powering on and off the TYVASO Inhalation System. ("On" / "Off", Symbol 5010 of IEC 60417 Database Snapshot - Graphical symbols for use on equipment)

Start/Pause. Indicates the control for starting a treatment session once the device is powered on, and for pausing a treatment once a treatment session has started. (Play and Pause, Symbols 5107B and 5111B, respectively, of IEC 60417 Database Snapshot - Graphical symbols for use on equipment)

D: Inhalation device display screens

Splash screen
Device name and software version

Last Treatment
Time since your last treatment

Program Breaths
Number of breaths set in Program mode

Adjust Volume
Audio volume level set in Run mode

Breaths Left
Number of breaths left in a current dose

Exhale
Prompt to exhale during a dose

Inhale
Prompt to inhale during a dose

Done
Treatment session is complete

Pause
You have paused a treatment session

Call Support
Device is not working, call your specialty pharmacy provider for support

Add Water
Wrong or missing fluid in water chamber

Charge Battery
Battery not charged enough to deliver treatment

Status icons
Icons that might appear at bottom of the screen

Programming your TYVASO Inhalation System before use

Section overview

This section provides instructions for charging your device, setting your dose, and adjusting the device's audio volume before you use the device for a treatment.

What you will need:

▶ A clean place to work with the device

▶ TYVASO Inhalation Device

▶ The number of breaths your doctor prescribed for each dose

What is covered in this section:
A: Charging device before use | 20
B: Setting your prescribed dose | 22
C: Adjusting device's audio volume | 24

Important:

Do not start treatment with TYVASO until you have been trained to use the TYVASO Inhalation System. Make sure you understand all of the directions. Always ask your doctor or specialty pharmacy provider if you have any questions or are unsure of anything you are taught.

A: Charging device before use

1. Plug in device

Important: A new device might not be fully charged when you receive it. Always charge the device before you first use it. You can also charge the device overnight, when not in use and in between uses.

Plug the AC wall plug's white connector into the port on the back of the inhalation device. Then, plug the AC wall plug into the wall outlet.

The power status light above the port will light green when properly plugged in.

2. Check the battery's status

Make sure the Run / Program switch is set to Run. Press and hold the blue button to power on the device.

The battery icon at the bottom of the screen indicates battery status.

When you are done checking the battery status, press and hold the On/Off button until the display screen shuts off (note: letting the button go before the screen shuts off will start a treatment session).

If there is not enough charge to conduct a treatment session, "Charge battery" appears on screen.

B: Setting your prescribed dose

Your doctor will prescribe the number of breaths you should take in each treatment session. You should program this number into the inhalation device before you use the device.

1. Switch to Program

Slide the Run / Program switch on the side of the device down to Program mode. In Program mode you enter the prescribed number of breaths for each dose. You cannot begin a treatment in Program mode.

2. Power on

Press and hold the On/Off button until the display screen turns on. The Program Breaths screen appears. The number of breaths currently set for each treatment session will flash.

3. Set breaths

Use the Volume / Breaths toggle button to enter your prescribed number of breaths onto the program screen.

4. Switch to Run

Slide the Run / Program switch up to Run mode. Make sure your new breath count appears on screen.

5. Power off

Press and hold the On/Off button until the display screen shuts off (note: letting the button go before the screen shuts off will start a treatment session).

Note: You will not need to program the breath count again, unless your prescribed number of breaths changes.

C: Adjusting device's audio volume

You can use the Volume / Breaths toggle button to adjust the volume of the audible signals (beeps) that the device provides as feedback during treatment sessions.

1. Switch to Run

Slide the Run / Program switch up to Run mode, if it is not in this position already.

2. Power on

Press and hold the On/Off button until the display screen turns on, if it is not already turned on. The programmed number of breaths will appear with the words "Breaths left" and the battery icon at the bottom.

3. Adjust volume

With the Run / Program switch in the Run position, press the Volume / Breaths toggle button to access the Adjust Volume screen. Push + on the Volume / Breaths toggle button to increase beeping volume, or push - to decrease beeping volume.

audio off

mid-level volume

maximum volume

4. Power off

After adjusting the beeping volume up or down, the screen will display your new setting for a couple of seconds then return to the screen displaying the breaths left.

Press and hold the On/Off button until the display screen shuts off (note: letting the button go before the screen shuts off will start a treatment session).

Preparing and using your TYVASO Inhalation System for daily treatments

Section overview

This section provides instructions for preparing and using your TYVASO Inhalation System for daily treatments.

What you will need:

▶ A clean place to take your medicine

▶ TYVASO Inhalation device

▶ TYVASO Inhalation supplies

▶ One ampule of TYVASO Inhalation Solution

What is covered in this section:
A: Prepare a proper environment | 28
B: Gather supplies | 29
C: Fill water chamber and medicine cup | 32
D: Assemble inhalation device | 35
E: Power on inhalation device | 40
F: Inhale your medicine | 42

Important:

Before using the TYVASO Inhalation System, you should:

- Wash your hands.
- Make sure the device is resting on a stable, flat surface during assembly.

A: Prepare a proper environment

Follow these important instructions before setting up your treatment:

- Use the device in a quiet, distraction-free area.
- Try to use the device at times when your treatment will not be interrupted. If needed, you can pause your treatment (see page 44).
- Use the device in a comfortable space where you can stand or sit in an upright position.
- Use the device in an area where you can access a power source if you need to use the AC wall plug.
- The TYVASO Inhalation System is recommended for use indoors.
- Use the device in an area that provides enough space for the TYVASO Inhalation System and its accessories.
- Gather all necessary supplies on a stable, flat surface for assembly (see page 29 for list of supplies).
- Store the inhalation device at 15°C to 30°C (59°F to 86°F). Use at 15°C to 25°C (59°F to 77°F).
- Use the device in a well-lit area where you can clearly read these instructions, labels on the device, and the device screen.

B: Gather supplies

Gather the following supplies before starting treatment. Use only the supplies provided in the starter kit and monthly refill kit for correct device function. Prior to use, inspect each part and do not use parts if they appear damaged or dirty.

Inhalation device
Powered off

TYVASO ampules
Use 1 ampule per day

Water level cup
with 45 mL of distilled water

Filter membranes [These accessories are replaced every month. Replacement accessories are included in the Monthly Refill Kit.]
Use 2 per day

Medicine cups
Use 1 per day

Dome assembly

Mouthpiece

Inhalation piece

2 filter shells

2 Plugs
(Used when storing the device)

Carrying case

Pen or pencil (not provided) to record your treatment

Distilled water carrier

AC wall plug

Treatment Tracker Example

C: Fill water chamber and medicine cup

Important:

- Wash your hands
- Unplug device when filling to avoid damage to cords or connectors.
- Only use distilled water in the device. Distilled water is highly purified water that is required for the device to function properly. If you use another type of water (such as bottled or tap water), the device might not function properly. You can purchase distilled water at most grocery stores and pharmacies.

1. Fill water chamber

Fill the water level cup with distilled water up to the arrow markers on the water cup. Use fresh distilled water each day (i.e., do not use water left in the water chamber from the previous day). Pour the distilled water into the water chamber.

Make sure the water level is above the upper, silver sensor and below the blue ring in the water chamber (about 45 mL of distilled water).

Do not overfill the water chamber, or else the medicine cup might not fit correctly.

2. Place medicine cup

Obtain 1 new medicine cup and inspect it. Do not use a medicine cup that is damaged (e.g., cracked or contains holes or dents), dirty, or was used before.

Place the empty medicine cup into the water chamber of the device, making sure that the cup's bottom tip is in the distilled water.

CAUTION: Make sure you place only 1 medicine cup. Placing multiple cups will prevent the flow of medicine.

3. Gather one ampule

Carefully cut open the top of the foil pouch, making sure not to cut the ampules. Each pouch contains 4 ampules. Remove 1 ampule of TYVASO.

Keep unused ampules in the foil pouch because the TYVASO medicine is sensitive to light. Write the date you first opened the pouch on the foil pouch.

One ampule contains enough medicine for 1 day of treatment no matter how many breaths your doctor has prescribed.

CAUTION: Ampules must be used within 7 days of opening foil pouch. Open only 1 pouch at a time. Throw away (discard) any unused ampules after 7 days.

4. Open ampule

Gently hold the ampule in the upright (top up) position and twist off its top.

CAUTION: If any medicine from the ampule spills on your hands, wash your hands right away. Medicine contact with the skin can cause irritation.

5. Squeeze ampule

Point the ampule straight down toward the medicine cup's center to avoid spills.

Gently squeeze the medicine out of the ampule into the medicine cup. Squeeze until it is empty. Check to see that all of the medicine is in the medicine cup.

D: Assemble inhalation device

Important: Do not force parts together.

The TYVASO Inhalation System is designed so the parts only fit together properly one way. When the device is assembled correctly, the parts should fit together easily.

1. Check dome assembly

Visually check to make sure the black ring is securely placed in the dome assembly. The black ring should look like it does in the pictures below.

If the black ring is loose or missing, do not use the dome assembly. Throw it away and get a new one. If you need to order a new dome assembly, contact your specialty pharmacy provider.

2. Attach dome assembly

Align the raised circle on the side of the dome assembly with the raised circle on the side of the device.

Push down and screw the dome assembly onto the device clockwise (right) until the filter shell port is tight and pointed to the back of the device. You will hear clicks (or a slight crunching sound) as the dome assembly presses down on the medicine cup.

Important: The dome assembly "clicks" only the first time it connects to the medicine cup. If you then realign the dome assembly you will not hear another click.

3. Install new filter membrane

Each day you will need to use a new filter membrane in each filter shell.

Note: New filter shells come with fresh filter membranes already installed.

To install a new filter membrane:

▶ a. Open the filter shell by unscrewing the 2 halves.

▶ b. Place a new filter membrane in 1 of the filter shell halves.

▶ c. Close the filter shell by screwing the 2 halves together until you can twist no further.

▶ d. Repeat steps a-c for second filter shell.

4. Attach filter shells

Insert 1 filter shell into the filter shell port on the side of the dome assembly and insert the second filter shell into the port on the bottom of the inhalation piece. The filter shells are the same and can be used in either port. You can turn the filter shells around to fit into the ports, as needed.

Make sure to insert filter shells straight into ports, not at an angle.

5. Insert inhalation piece

Insert the inhalation piece with attached filter shell into the upper opening of the dome assembly and turn it toward the front of the device. Gently push down the inhalation piece to make sure it is securely inserted in the dome assembly.

6. Insert mouthpiece

Carefully insert the mouthpiece into the inhalation piece.

7. Check assembled device

When the device is fully assembled, it should look like it does below. Slightly turn the inhalation piece so you can see the display screen, which provides important prompts during your treatment.

Important: Do not use device if you see liquid leaking from bottom of the device.

E: Power on inhalation device

1. Power on device

Press and hold the On/Off button until the screen turns on and the device beeps once.

The screen will display the splash screen, then the time since your last treatment, then the current breaths programmed for each dose.

Important: Make sure the number on screen above "Breaths left" matches the prescribed number of breaths for that treatment session. If it does not match, see page 22 for instructions on setting the number of breaths for a treatment session.

2. Plug in device, if needed

If the device's internal battery is too low to deliver a full treatment, the screen will display an instruction to plug in the power to charge the device battery. If the battery is fully depleted, the screen will not turn on.

You can charge the battery at any time, before the screen displays "Charge battery."

You can conduct a treatment session with the power plugged in. First, plug the AC wall plug's white connector into the port on the back of the inhalation device. Then, plug the AC wall plug into the wall outlet. The power status light above the port will light green when properly plugged in.

F: Inhale your medicine

1. Before starting, confirm treatment

You will breathe in (inhale) TYVASO during 4 treatment sessions each day (evenly spaced during your waking hours). During each treatment session, you will take a series of breaths through the mouthpiece of the TYVASO Inhalation System.

Before inhaling your medicine, ensure the Run/Program switch is in the 'Run' position, and make sure the number displayed on screen matches your prescribed number of breaths for that treatment session. During the treatment the device counts down each breath after a set time interval. Once you complete all breaths, record the breath number in your Treatment Tracker.

Important: If the number of breaths displayed does not match the number of breaths in your prescription, see page 22 "Setting your prescribed dose" and repeat steps 1-4.

2. Hold the device upright

Hold the device upright and stand or sit in an upright position as shown below. Avoid covering the bottom of the device so that the audio speaker is not blocked.

Make sure you can see the display screen and lights clearly and that your hands do not cover the display screen or lights while holding device. If needed, you can move the inhalation piece and mouthpiece slightly to either side to see the screen and lights better.

See next page to start treatment.

Inhalation tips:

Technique:

When breathing each TYVASO treatment, be sure to keep the device level, directing the flow of medicine into the throat and not toward the roof of the mouth.

Seal your lips around the mouthpiece to ensure that you can inhale the full amount of TYVASO after it is produced by the device.

Inhalation:

Each breath should last approximately 3 seconds, breathing "normal full breaths." Do not hold your breath. Remove your lips from the mouthpiece, breathe out (exhale) normally and prepare for the next breath.

3. Press blue button to start treatment

If you need to pause treatment, you can press and immediately release (do not hold down) the blue button. Press the button again and immediately release to resume treatment. (Note: If you do not resume treatment after pausing, power off device.)

4. Wait

Look at the display screen for cues. Wait until you hear 2 short beeps. When you hear 1 long beep, exhale to prepare to inhale.

5. Inhale

When you hear 1 short beep and the indicator lights flash green, place your lips securely around the mouthpiece and inhale for 3 seconds. When lights stop flashing, remove lips from mouthpiece and exhale normally.

6. Repeat for each breath left

The screen will decrease the number of breaths left by 1. Repeat steps 4 and 5 for the number of prescribed breaths.

7. Finish session

After displaying the last breath sequence, the green Done screen appears, you will hear a beep, and your treatment is done.

If the device is left in the "✓ Done" mode for more than 60 seconds, it will turn off automatically.

8. Record breaths, turn off device

Record the number of breaths you inhaled on the Treatment Tracker.

Press and hold blue button until screen turns off.

CAUTION: If medicine does not appear to be flowing properly, the system might be set up incorrectly. See "Troubleshooting", starting on page 64 for details.

Cleaning and Storing your TYVASO Inhalation System

Section overview

This section provides instructions for storing your TYVASO Inhalation System after each treatment and daily and weekly cleaning.

There is also information about your monthly refill kits, replacing your device, and recharging the device's battery.

What you will need:

▶ A clean place to work with the device

▶ TYVASO Inhalation device

▶ TYVASO Inhalation supplies

What is covered in this section:
A: Storing between sessions during the day | 48
B: End of day cleaning | 52
C: Recharging the battery | 57
D: Weekly cleaning | 59
E: Monthly Refill Kit | 60
F: Replacing your devices | 61

Important:

For further support, you can:

- Fill out and refer to your emergency contact information on the back of this Instructions for Use manual.
- Call 1-877-UNITHER (1-877-864-8437) for questions and information, or to report an adverse reaction.

A: Storing between sessions during the day

If you have more treatment sessions left in the day, perform the steps in this section.

If you have completed your last treatment session of the day, skip to "End of day cleaning" on page 52.

Be sure to pack all parts, including the AC wall plug, in the carrying case whenever transporting your device.

1. Disconnect AC wall plug
(if it is currently connected)

2. Remove mouthpiece

3. Remove inhalation piece

Important: When removing accessories between treatment sessions, hold the device by its base to avoid spilling the medicine.

4. Remove both filter shells

Note: Do not remove the filter membranes from filter shells until after the last treatment session of the day.

5. Leave dome assembly

Leave dome assembly and medicine cup (with the medicine still in it) attached to the device.

6. Place plugs in dome assembly

Insert a plug into each of the 2 open holes on the dome assembly to prevent the medicine from spilling out.

Important: If the plugs are not in place, the medicine may spill. If you spill any medicine, discard remaining medicine and start your next treatment with a new ampule.

7. Store in carrying case

You can store the inhalation device with the plugged dome assembly and disassembled accessories in the carrying case between treatment sessions.

Keep the carrying case upright while inserting the device and components so that water and medicine does not spill out of the device.

Important: Store the inhalation device in an upright position until the next treatment session. See "Specifications" on page 76 for additional storage and transport information.

B: End of day cleaning

If you have completed your last treatment session of the day, perform the steps in this section.

If you have more treatment sessions left in the day, refer back to "Storing between sessions during the day" on page 48.

1. Disconnect AC wall plug
(if it is currently connected)

2. Remove mouthpiece

3. Remove inhalation piece with attached filter shell

4. Remove both filter shells

5. Discard filter membranes

Open filter shells by twisting in opposite directions. Remove and discard used filter membranes in the trash.

6. Remove dome assembly

Remove the dome assembly by turning it counter-clockwise (to the left). The medicine cup should stay attached to the dome assembly.

7. Remove medicine cup

Remove the medicine cup by gently squeezing on the sides where it is attached to the dome assembly.

Be careful not to spill any leftover medicine.

CAUTION: If any medicine from the medicine cup spills on your hands, wash your hands immediately. Medicine contact with the skin can cause irritation.

8. Empty medicine cup

Empty any leftover medicine in the medicine cup into a waste basket, and discard the medicine cup.

Important: Discard remaining TYVASO® (treprostinil) Inhalation Solution in an appropriate waste receptacle. Discard plastic medicine cup in the trash.

Do not reuse or recycle medicine cup.

9. Empty and clean device

Empty distilled water from water chamber and let inhalation device air dry upside down. You can wipe the water chamber with a soft cloth or paper towel to remove any remaining water.

Important: Do not place the inhalation device in water or in a dishwasher.

10. Clean accessories

Clean accessories (pictured below) by hand in mild, soapy, warm water, then rinse them thoroughly with water. Allow accessories to air dry.

Dome assembly

Inhalation piece

Mouthpiece

Filter shells

Important: Do not place the inhalation device or its accessories in a microwave, conventional oven, or dishwasher.

11. Store components

Once all the items are dry, you can store the filter shells, inhalation piece, mouthpiece, dome assembly, AC wall plug, and inhalation device in the carrying case until the next day's treatment sessions.

You can also recharge the device for the next day of use (see page 57).

C: Recharging the battery

1. Checking the battery's status

You can recharge your battery at any time. Press and hold the blue button to power on the device to check battery status. Make sure the Run / Program switch is set to Run.

- The battery icon at the bottom of the screen indicates battery status:

- "Charge battery" appears on screen if there is not enough charge to conduct a treatment session.

Important: Always charge the device before you first use it. You should also charge the device when not in use and in between uses.

2. Charging the battery

Plug the AC wall plug's white connector into the port on the back of the inhalation device. Then, plug the AC wall plug into the wall outlet. The power status light above the port will light green when properly plugged in.

The device battery might take up to 8 hours to fully charge.

If the device is powered on, the battery charging icon appears next to the battery icon at the bottom of the screen.

Battery charging icon

D: Weekly cleaning

Clean the device once a week to help avoid corrosion and leaks and to keep your device working properly.

Once a week, use a clean, dry cloth to wipe the interior of the water chamber. Make sure to wipe the 2 silver sensors and the white disc in the bottom of the water chamber.

You may wipe the exterior of the device with a damp cloth if the lights or buttons become difficult to see.

E: Monthly Refill Kit

Once a month, you will receive a refill kit that will come with a new set of accessories from your specialty pharmacy provider.

- Inspect the shipment to be sure all parts are included.
- Once the new kit has arrived, discard the used dome assembly, inhalation piece, mouthpiece, filter shells, and plugs.
- Do not recycle the used accessories.

Dome assembly

2 filter shells

Mouthpiece

Inhalation piece

2 plugs

Filter membranes

Medicine cups

F: Replacing your devices

The inhalation devices should be replaced every 2 years from your first day of use. Replacement inhalation devices will be supplied by your specialty pharmacy provider.

When you receive a new inhalation device your specialty pharmacy provider will provide instructions for returning the old device.

Help / More information about your TYVASO Inhalation System

Section overview

This section provides additional information about your device. Use this section to troubleshoot difficulties you have with the device, or to learn more about the device's specifications and warranty.

What you will need:

▶ Access to a phone (to contact support if troubleshooting steps do not resolve the problem)

▶ A clean place to work with the device

▶ TYVASO Inhalation Device or supplies, as needed

What is covered in this section:
A: Troubleshooting | 64
B: Specifications | 76
C: Electromagnetic compatibility (EMC) | 79
D: Glossary | 87
E: Warranty information | 90

Important:

For further support, you can:

- Fill out and refer to your emergency contact information on the back of this Instructions for Use manual.
- Call 1-877-UNITHER (1-877-864-8437) for questions and information, or to report an adverse reaction.

A: Troubleshooting

Problem | Possible causes | Corrective actions
Charge Battery screen appears | Low battery | Charge the device battery by attaching the AC wall plug to an outlet. You can conduct a treatment session with the device plugged in.
Charge Battery screen appears | AC wall plug not properly connected | Ensure that the plug adapter piece (the detachable piece with the metal prongs) is securely attached to the AC wall plug. Then, make sure the AC wall plug is properly connected to an outlet and device. The status lights on the back of the AC wall plug and device should light green. You can conduct a treatment session with the device plugged in.
Charge Battery screen appears | AC wall plug is defective | Use the replacement AC wall plug. Confirm that status light on AC wall plug is green when plugged in. You can conduct a treatment session with the device plugged in.
Charge Battery screen appears | If device still does not function after taking corrective actions listed above, contact your specialty pharmacy provider for assistance.
Screen does not turn on | Device battery is completely empty | Charge the device battery by attaching the AC wall plug to an outlet. You can conduct a treatment session with the device plugged in.
Screen does not turn on | AC wall plug not properly connected | Ensure that the plug adapter piece (the detachable piece with the metal prongs) is securely attached to the AC wall plug. Then, make sure the AC wall plug is properly connected to an outlet and device. The status lights on the back of the AC wall plug and device should light green. You can conduct a treatment session with the device plugged in.
Screen does not turn on | AC wall plug is defective | Use the replacement AC wall plug. Confirm that status light on AC wall plug is green when plugged in. You can conduct a treatment session with the device plugged in.
Screen does not turn on | If device still does not function after taking corrective actions listed above, contact your specialty pharmacy provider for assistance.
Call Support screen appears | Temporary device failure. | If device is plugged in, unplug device and wait for the device to power off. Power on device from internal battery and check that Call Support screen does not reappear. Continue taking breaths to complete the treatment session.
Call Support screen appears | If device still does not function after taking corrective actions listed above, contact your specialty pharmacy provider for assistance.
Loss of power during treatment | Device is disconnected from power source and battery is empty | Reconnect device to power source and confirm the power status light on back of device is green (battery is charging). Press and hold the blue On/Off button to turn on the device. The display will show how many breaths are left in that treatment session. Press and immediately release (do not hold down) the blue button again to continue your treatment session.
Loss of power during treatment | Power source is temporarily disrupted (for example, electricity interruption due to a storm) | Reconnect device to power source and confirm the power status light on back of device is green (battery is charging). Press and hold the blue On/Off button to turn on the device. The display will show how many breaths are left in that treatment session. Press and immediately release (do not hold down) the blue button again to continue your treatment session.
Loss of power during treatment | If device still does not function after taking corrective actions listed above, contact your specialty pharmacy provider for assistance.
Add Water screen appears | Water chamber is empty or distilled water level is too low. | Unplug device, if plugged in, and power off device. Remove dome assembly (making sure not to spill medicine) and place it aside, keeping it upright. Then empty water chamber. Refill water chamber with distilled water using water level cup (see page 32). Reassemble device. Power the device on and continue treatment.
Add Water screen appears | The distilled water is too pure. | Unplug device, if plugged in, and power off device. Remove dome assembly (making sure not to spill medicine) and place it aside, keeping it upright. Then empty water chamber. Add 1 teaspoon of tap water to the water level cup. Fill rest of cup with distilled water up to level between the 2 arrow markings on cup (see page 32). Pour cup's contents into water chamber. Reassemble device. Power the device on and continue treatment.
Add Water screen appears | Water level sensors have a thin layer of build-up | Unplug device, if plugged in, and power off device. Remove dome assembly (making sure not to spill medicine) and place it aside, keeping it upright. Then empty water chamber. Clean sensors and interior surfaces of water chamber with a clean cloth. Refill water chamber with distilled water using water level cup (see page 32). Reassemble device. Power the device on and continue treatment.
Add Water screen appears | If device still does not function after taking corrective actions listed above, contact your specialty pharmacy provider for assistance.
No "click" (or crunch) was heard when attaching the dome assembly | No medicine cup in the water chamber of the device | Unplug device, if plugged in, and power off device. Place an empty medicine cup into the water chamber of the device and fill it with 1 ampule of TYVASO. Reassemble device. Power the device on and continue treatment.
No "click" (or crunch) was heard when attaching the dome assembly | Multiple medicine cups attached to the dome assembly | Unplug device, if plugged in, and power off device. Remove and dispose of all medicine cups in the device. Place a single, new medicine cup into device water chamber and fill with 1 ampule of TYVASO. Reassemble device. Power the device on and continue treatment.
No "click" (or crunch) was heard when attaching the dome assembly | Dome assembly is not securely in place | Unplug device, if plugged in, and power off device. Align the raised circle on the side of the dome assembly with the raised circle on the side of the device.
No "click" (or crunch) was heard when attaching the dome assembly |  | Push down and screw the dome assembly onto the device clockwise (right) until the filter shell port is tight and pointed to the back of the device and the raised circles line up again. You will hear clicks (or crunch sound) as the dome assembly presses down on the medicine cup. Reassemble device. Power the device on and continue treatment.
No "click" (or crunch) was heard when attaching the dome assembly | If device still does not function after taking corrective actions listed above, contact your specialty pharmacy provider for assistance.
No medicine comes out of the device during a treatment session | No TYVASO® (treprostinil) Inhalation Solution in the medicine cup | Unplug device, if plugged in, and power off device. Fill medicine cup with 1 ampule of TYVASO. Reassemble device. Power the device on and continue treatment.
No medicine comes out of the device during a treatment session | Damaged medicine cup | Unplug device, if plugged in, and power off device. Remove and dispose of the medicine cup in the device. Empty the water chamber then refill it with 45 mL of distilled water (see page 32). Place a single, new medicine cup into water chamber and fill with 1 ampule of TYVASO. Reassemble device. Power the device on and continue treatment.
No medicine comes out of the device during a treatment session | Distilled water level in the water chamber is too high | Unplug device, if plugged in, and power off device. Remove dome assembly (making sure not to spill medicine) and place it aside, keeping it upright. Empty the water chamber then refill it with 45 mL of distilled water (see page 32). Reassemble device. Power the device on and continue treatment.
No medicine comes out of the device during a treatment session | Multiple medicine cups attached to the dome assembly | Unplug device, if plugged in, and power off device. Remove and dispose of all medicine cups in the device. Place a single, new medicine cup into water chamber and fill with 1 ampule of TYVASO. Reassemble device. Power the device on and continue treatment.
No medicine comes out of the device during a treatment session | If device still does not function after taking corrective actions listed above, contact your specialty pharmacy provider for assistance.
Difficult to breathe in medicine through the mouthpiece | Filter membrane is clogged | Unplug device, if plugged in, and power off device. Replace both filter membranes (see page 37). Reassemble device. Power the device on and continue treatment.
Difficult to breathe in medicine through the mouthpiece | If device still does not function after taking corrective actions listed above, contact your specialty pharmacy provider for assistance.

B: Specifications

Inhalation Device
Model | TD-300/A
Size | 3.5" × 3.2" × 4.7" (90 × 82 × 120 mm)
Weight, inhalation device | 365 g (12.8 oz)
Types of power supply | AC wall plug, 120 V, 60 Hz
Power input | 14 V DC, 1.1 A maximum
Operating power consumption | 18 Watt maximum
Ultrasonic frequency | 2.4 MHz (nominal)
Nebulization rate | 0.50 - 0.55 mg/min (0.9% Saline)
Medicine cup capacity | 6 mL, nominal
Water chamber capacity | 45 mL, nominal
Electric protection class | II, Type BF
Storage temperature/humidity | 15 to 30ºC/20-80% relative humidity
Operating temperature/humidity | 15 to 25ºC/40-75% relative humidity
A-weighted sound pressure level | 75 dBA (1 m), maximum

Packaging Dimensions (Approximate Length × Width × Height)
Patient Starter Kit (PSK) | 13.0" × 12.4" × 9.2"
Monthly Refill Kit (MRK) | 11.8" × 8.2" × 3.0"
Institutional Starter Kit (ISK) | 13.0" × 12.4" × 9.2"

TYVASO Mass and Particle Specifications for 9 breaths
Mass Median Aerodynamic Diameter (MMAD) [n=108 data points from r=3 inhalation devices. Each data point was 9 breaths.] | mean = 2.0 µm SD = 0.3
Total Emitted Dose per Breath [n=216 data points from r=6 inhalation devices. Each data point was 1 breath.] | mean = 6.0 µg SD = 0.4
Total Aerosol Mass | mean = 58 µg SD = 5.9
Total Respirable Dose | mean = 44.6 µg SD = 3.5
Respirable Fraction | mean = 73% SD = 5
Geometric Standard Deviation (GSD) | mean = 2.6 SD = 0.4

Accessories
TD-300N-US | AC wall plug
TD-132 | Medicine cup, Quantity - 32
ON-109 | Filter membranes
ON-120/C | Plugs
ON-101/C | Filter shell
TD-103/C | Dome assembly with baffle plate
ON-104/C | Inhalation piece
ON-105/C | Mouthpiece
TD-118 | Water level cup
TD-158 | Carrying case
TD-155 | Distilled water carrier
Note: Part number subject to change.

C: Electromagnetic compatibility (EMC)

The TYVASO Inhalation System has been tested and found to comply with the electromagnetic compatibility (EMC) limits for medical devices according to IEC 60601-1-2: (2007). Compliance is intended to provide reasonable protection against harmful interference in a typical user environment.

Table 1, Table 2 and Table 3 document the intended EMC use environment and established compliance levels for the TYVASO Inhalation System. To ensure the intended performance, use the system in the environments described in these tables.

The TYVASO Inhalation System is intended for use in the electromagnetic environment specified in this section.

Table 1: Guidance and manufacturer's declaration - electromagnetic emissions
Guidance and manufacturer's declaration - electromagnetic emissions
The TYVASO Inhalation System is intended for use in the electromagnetic environment specified below. The customer or the user of the TYVASO Inhalation System should assure that it is used in such an environment.
Emissions test | Compliance | Electromagnetic environment - guidance
RF emissions CISPR 11 | Group 1 | The TYVASO Inhalation System uses RF energy only for its internal function. Therefore, its RF emissions are very low and are not likely to cause any interference in nearby electronic equipment.
RF emissions CISPR 11 | Class B | The TYVASO Inhalation System is suitable for use in all establishments, including domestic establishments and those directly connected to the public low voltage power supply network that supplies buildings used for domestic purposes.
Harmonic emissions IEC 61000-3-2 | Class A | The TYVASO Inhalation System is suitable for use in all establishments, including domestic establishments and those directly connected to the public low voltage power supply network that supplies buildings used for domestic purposes.
Voltage fluctuations/flicker emissions IEC 61000-3-3 | Complies | The TYVASO Inhalation System is suitable for use in all establishments, including domestic establishments and those directly connected to the public low voltage power supply network that supplies buildings used for domestic purposes.

Table 2: Guidance and manufacturer's declaration – electromagnetic immunity
Guidance and manufacturer's declaration – electromagnetic immunity
The TYVASO Inhalation System is intended for use in the electromagnetic environment specified below. The customer or the user of the TYVASO Inhalation System should assure that it is used in such an environment.
Immunity test | IEC 60601 Test level | Compliance level | Electromagnetic environment - guidance
Electrostatic discharge (ESD) IEC 61000-4-2 | ± 8 kV contact ± 15 kV air | ± 8 kV contact ± 15 kV air | Floors should be wood, concrete or ceramic tile. If floors are covered with synthetic material, the relative humidity should be at least 30%.
Electrical fast transient/burst IEC 61000-4-4 | ± 2 kV for power supply lines ± 1 kV for input/output lines | ± 2 kV for power supply lines ± 1 kV for input/output lines | Mains power quality should be that of a typical commercial or hospital environment.
Surge IEC 61000-4-5 | ± 1 kV line(s) to line(s) ± 2 kV line(s) to earth | ± 1 kV line(s) to line(s) ± 2 kV line(s) to earth | Mains power quality should be that of a typical commercial or hospital environment.
Voltage dips, short interruptions and voltage variations on power supply input lines IEC 61000-4-11 | 0 % UT (100 % dip in UT) for 0,5 cycle 0 % UT (100 % dip in UT) for 1 cycle 70 % UT (30 % dip in UT) for 25/30 cycles 0 % UT (100 % dip in UT) for 250/300 cycle | 0 % UT (100 % dip in UT) for 0,5 cycle 0 % UT (100 % dip in UT) for 1 cycle 70 % UT (30 % dip in UT) for 25/30 cycles 0 % UT (100 % dip in UT) for 250/300 cycle | Mains power quality should be that of a typical commercial or hospital environment. If the user of the TYVASO Inhalation System requires continued operation during power mains interruptions, it is recommended that the TYVASO Inhalation System be powered from an uninterruptible power supply or the internal battery.
Power frequency (50/60 Hz) magnetic field IEC 61000-4-8 | 30 A/m | 30 A/m | Power frequency magnetic fields should be at levels characteristic of a typical location in a typical commercial or hospital environment.
Conducted RF IEC 61000-4-6 Radiated RF IEC 61000-4-3 | 3 Vrms 150 kHz to 80 MHz 10 V/m 80 MHz to 2.6 GHz | 3 Vrms 150 kHz to 80 MHz 10 V/m 80 MHz to 2.6 GHz | Portable and mobile RF communications equipment should be used no closer to any part of TYVASO Inhalation System, including cables, than the recommended separation distance calculated from the equation applicable to the frequency of the transmitter. Recommended separation distance d = 1.2 √P d = 1.2 √P 80 MHz to 800 MHz d = 2.3 √P 800 MHz to 2.5 GHz where P is the maximum output power rating of the transmitter in watts (W) according to the transmitter manufacturer and d is the recommended separation distance in meters (m). Field strengths from fixed RF transmitters, as determined by an electromagnetic site survey [Field strengths from fixed transmitters, such as base stations for radio (cellular/cordless) telephones and land mobile radios, amateur radio, AM and FM radio broadcast and TV broadcast cannot be predicted theoretically with accuracy. To assess the electromagnetic environment due to fixed RF transmitters, an electromagnetic site survey should be considered. If the measured field strength in the location in which the TYVASO Inhalation System is used exceeds the applicable RF compliance level above, the TYVASO Inhalation System should be observed to verify normal operation. If abnormal performance is observed, additional measures may be necessary, such as re-orienting or relocating the TYVASO Inhalation System.] , should be less than the compliance level in each frequency range [Over the frequency range 150 kHz to 80 MHz, field strengths should be less than [V1] V/m.] . Interference may occur in the vicinity of equipment marked with the following symbol:
NOTE: UT is the a.c. mains voltage prior to application of the test level.
NOTE 1: At 80 MHz and 800 MHz, the higher frequency range applies.
NOTE 2: These guidelines may not apply in all situations. Electromagnetic propagation is affected by absorption and reflection from structures, objects and people.

Table 3: Manufacturer's Declaration – Recommended separation distances between portable and mobile communications equipment and the TYVASO Inhalation System
Recommended separation distances between portable and mobile RF communications equipment and the TYVASO Inhalation System
The TYVASO Inhalation System is intended for use in an electromagnetic environment in which radiated RF disturbances are controlled. The customer or the user of the TYVASO Inhalation System can help prevent electromagnetic interference by maintaining a minimum distance between portable and mobile RF communications equipment (transmitters) and the TYVASO Inhalation System as recommended below, according to the maximum output power of the communications equipment.
Rated maximum output power of transmitter W | Separation distance according to frequency of transmitter m
Rated maximum output power of transmitter W | 150 kHz to 80 MHz d = 1.2 √P | 80 MHz to 800 MHz d = 1.2 √P | 800 MHz to 2.5 GHz d = 2.3 √P
0.01 | 0.12 | 0.12 | 0.23
0.1 | 0.38 | 0.38 | 0.73
1 | 1.2 | 1.2 | 2.3
10 | 3.8 | 3.8 | 7.3
100 | 12 | 12 | 23
For transmitters rated at a maximum output power not listed above, the recommended separation distance d in meters (m) can be estimated using the equation applicable to the frequency of the transmitter, where P is the maximum output power rating of the transmitter in watts (W) according to the transmitter manufacturer.
NOTE 1: At 80 MHz and 800 MHz, the separation distance for the higher frequency range applies.
NOTE 2: These guidelines may not apply in all situations. Electromagnetic propagation is affected by absorption and reflection from structures, objects and people.

D: Glossary

Accessories: Parts of the TYVASO Inhalation System. See page 29.

Ampule: A sealed, lightweight clear plastic vial containing a 1-day supply of TYVASO® (treprostinil) Inhalation Solution.

Black ring: A round seal that fits on the bottom of the dome assembly. The seal helps ensure that TYVASO does not mix with the distilled water in the device water chamber.

Display screen: A small area on the inhalation device that provides instructions and device information.

Distilled water: Water that is highly purified so that it contains only essential elements.

Dome assembly: The plastic accessory that contains the baffle plate and connects the mouthpiece, inhalation piece, and filter shells to the base of the inhalation device.

Filter membrane: The white pad that goes into the filter shells.

Filter shells: Plastic accessories that hold the filter membranes.

Inhalation indicator lights: Two green lights on the top surface of the inhalation device that signals when you should inhale.

Inhalation piece: The plastic accessory that connects the mouthpiece with the dome assembly.

Inhalation device: The base of the TYVASO Inhalation System to which the accessories connect. The inhalation device contains the display screen and lights.

Inhale: How you will breathe in TYVASO with the TYVASO Inhalation System.

Medicine cup: The disposable plastic cone-shaped cup into which TYVASO is poured. The medicine cup fits inside the water chamber.

Mouthpiece: The plastic part that you will breathe through (using your mouth) to inhale TYVASO.

On/Off, Start/Pause (blue) button: A manually activated control on the front of the device that switches between fully on and fully off power states. Once the device power is on, the button begins or pauses treatment.

Plugs: Plastic accessories that are inserted into the openings of the dome assembly between treatment sessions. Plugs help keep TYVASO from spilling if the inhalation device tips over.

Power status light: LED on the back of the device that lights green when power is connected and battery is charging.

Power port: Port on back of device for plugging into a power source using the AC wall plug.

Prompts: The audio and visual signals that help guide you through the treatment sessions.

Run / Program switch: A manually activated control on the side of the device that switches between the modes for delivering treatment (Run) and programming breaths (Program).

Sensors: The silver objects on the inside wall of the water chamber. The sensors must be covered with distilled water for the TYVASO Inhalation System to function properly.

Specialty pharmacy provider: A pharmacy that carries only specialized medicines and medical devices. Your specialty pharmacy provider is a good source of information about TYVASO and the TYVASO Inhalation System.

Treatment session: 1 of 4 daily sessions during which you will take TYVASO with a specific number of inhalations.

TYVASO: The prescription medicine that you will use with the TYVASO Inhalation System.

Volume / Breaths toggle button: A manually activated control on the side of the device that increases or decreases audio volume (when in Run mode) and programmed breaths (when in Program mode).

Water chamber: The white hollow portion in the center of the inhalation device into which distilled water and the medicine cup are placed.

E: Warranty information

Your TYVASO Inhalation System is granted a replacement or repair warranty good for 2 years from your date of receipt of the TYVASO Inhalation System or 5 years from the date of manufacture, whichever comes first. This warranty applies to the TYVASO Inhalation System device only. Accessory components are not covered under warranty.

Circumstances that may void your warranty include:

▶ Modification or disassembly of the TYVASO Inhalation System device by anyone other than a factory-authorized technician

▶ Failure to comply with this written Instructions for Use manual when operating the TYVASO Inhalation System

▶ Unapproved use of the TYVASO Inhalation System

For all inquiries relating to service or warranty for your TYVASO Inhalation System, contact your specialty pharmacy provider.

You should have the following information available:

▶ Device serial number (located on bottom of TYVASO Inhalation System)

▶ Date TYVASO Inhalation System was acquired

▶ Nature of the problem and any steps taken to fix it

TYVASO ®
INHALATION SYSTEM

TYVASO®
(treprostinil)
INHALATION
SOLUTION

TYVASO Inhalation Solution is for prescription use only.

Emergency contact information

▶ Clinician:

▶ Nurse educator:

▶ Specialty pharmacist:

▶ United Therapeutics:

For further questions and information, or to report a problem with your device or an adverse event with your TYVASO Inhalation System, please call 1-877-UNITHER (1-877-864-8437).

Distributed by:
United Therapeutics Corporation
Research Triangle Park, North Carolina 27709

© 2024, United Therapeutics Corporation.
All rights reserved.

102131

TYVASO is a registered trademark of
United Therapeutics Corporation.

This Instructions for Use has been
approved by the U.S. Food and Drug
Administration.

Revised: January 2024

PRINCIPAL DISPLAY PANEL - 4 Ampule Pouch Carton

TYVASO®
(treprostinil)
INHALATION
SOLUTION

Treprostinil 1.74 mg / 2.9 mL (0.6 mg/mL)

Four 2.9 mL ampules

For oral inhalation use only

See package insert and
Instructions For Use manual
for dosage and administration

PRINCIPAL DISPLAY PANEL - 28 Ampule Pouch Carton

TYVASO®
(treprostinil)
INHALATION
SOLUTION

Treprostinil 1.74 mg / 2.9 mL (0.6 mg/mL)

Seven foil pouches each containing four
2.9 mL ampules

For oral inhalation use only

See package insert and
Instructions For Use manual
for dosage and administration.

PRINCIPAL DISPLAY PANEL - Patient Starter Kit

TYVASO Inhalation System

Patient Starter Kit

TYVASO®
(treprostinil)
INHALATION
SOLUTION

Treprostinil 1.74 mg/2.9 mL (0.6 mg/mL)

TYVASO is for oral inhalation use only and is intended for administration with the TYVASO Inhalation System.
See package insert and Instructions for Use manual for dosage and administration.

CONTENTS | QTY | CONTENTS | QTY
+ 28 ampule carton of TYVASO (seven foil pouches, each containing four 2.9 mL ampules) | 1 | + AC wall plugs | 2
+ TYVASO Inhalation Device | 2 | + Water level cup | 1
+ TYVASO Inhalation System Instructions for Use manual | 1 | + Plugs for storage between treatment sessions | 2
+ Treatment Tracker | 1 | + Carrying case | 1
+ Sets of Dome assembly, Inhalation piece, Mouthpiece, and 2 Filter shells | 2 | + Distilled water carrier | 1
+ Medicine cups | 32 | + Filter membranes | 65

Each ampule of TYVASO contains: treprostinil 1.74 mg. Each ampule also contains 18.9 mg sodium chloride,
18.3 mg sodium citrate dihydrate, 0.6 mg sodium hydroxide, 11.7 mg 1N hydrochloric acid, and water for injection.
Hydrochloric acid and sodium hydroxide may have been added to adjust pH.

+ One new ampule should be used each day. Each ampule of TYVASO (once opened and transferred to the
  medicine cup) should remain in the device for no more than 1 day. Any remaining TYVASO and the medicine
  cup should be discarded at the end of each day.
+ Once a foil pouch is opened, use ampules within 7 days.
+ Store unused ampules of TYVASO in the foil pouch until use, protected from light.
+ Store at 25°C (77°F); excursions permitted to 15°C to 30°C (59°F to 86°F) [see USP Controlled Room Temperature].

Patient Starter Kit For Single Patient Use Only.
Keep out of the reach of children.
NDC 66302-206-01
Rx only

Manufactured by United Therapeutics Corporation
Research Triangle Park, NC 27709

United
Therapeutics
CORPORATION

102129
Rev. 01/2024

PRINCIPAL DISPLAY PANEL - Refill Kit

TYVASO Inhalation System
Refill Kit

TYVASO®
(treprostinil)
INHALATION
SOLUTION

Treprostinil 1.74 mg/2.9 mL (0.6 mg/mL)

TYVASO is for oral inhalation use only and is intended for administration with the TYVASO Inhalation System.
See package insert and Instructions for Use manual for dosage and administration.

CONTENTS | QTY | CONTENTS | QTY
+ 28 ampule carton of TYVASO (seven foil pouches each containing four 2.9 mL ampules) | 1 | + Filter membranes | 65
+ Set of Dome assembly, Inhalation piece, Mouthpiece, and 2 Filter shells | 1 | + Plugs for storage between treatment sessions | 2
+ Medicine cups | 32 | + Treatment Tracker | 1

Each ampule of TYVASO contains: treprostinil 1.74 mg. Each ampule also contains 18.9 mg sodium chloride,
18.3 mg sodium citrate dihydrate, 0.6 mg sodium hydroxide, 11.7 mg 1N hydrochloric acid, and water for injection.
Hydrochloric acid and sodium hydroxide may have been added to adjust pH.

+ One new ampule should be used each day. Each ampule of TYVASO (once opened and transferred to the medicine
  cup) should remain in the device for no more than 1 day. Any remaining TYVASO and the medicine cup should be
  discarded at the end of each day.
+ Once a foil pouch is opened, use ampules within 7 days.
+ Store unused ampules of TYVASO in the foil pouch until use, protected from light.
+ Store at 25°C (77°F); excursions permitted to 15°C to 30°C (59°F to 86°F) [see USP Controlled Room Temperature].

Keep out of the reach of children.

NDC 66302-206-02
Rx only

Manufactured for United Therapeutics Corporation
Research Triangle Park, NC 27709

United
Therapeutics
CORPORATION

102136
Rev. 01/2024

LOT XXXXXXX
EXP YYYY-MMM
GTIN XXXXXXXXXXXXXX
S/N XXXXXXXXXXXX

PRINCIPAL DISPLAY PANEL - Institutional Starter Kit

TYVASO Inhalation System
Institutional Starter Kit

TYVASO®
(treprostinil)
INHALATION
SOLUTION

Treprostinil 1.74 mg/2.9 mL (0.6 mg/mL)

TYVASO is for oral inhalation use only and is intended for administration with the TYVASO Inhalation System.
See package insert and Instructions for Use manual for dosage and administration.

CONTENTS | QTY | CONTENTS | QTY
+ 4 ampule carton of TYVASO (one foil pouch containing four 2.9 mL ampules) | 1 | + AC wall plugs | 2
+ TYVASO Inhalation Device | 2 | + Water level cup | 1
+ TYVASO Inhalation System Instructions for Use manual | 1 | + Plugs for storage between treatment sessions | 2
+ Treatment Tracker | 1 | + Carrying case | 1
+ Sets of Dome assembly, Inhalation piece, Mouthpiece, and 2 Filter shells | 2 | + Distilled water carrier | 1
+ Medicine cups | 32 | + Filter membranes | 65

Each ampule of TYVASO contains: treprostinil 1.74 mg. Each ampule also contains 18.9 mg sodium chloride,
18.3 mg sodium citrate dihydrate, 0.6 mg sodium hydroxide, 11.7 mg 1N hydrochloric acid, and water for injection.
Hydrochloric acid and sodium hydroxide may have been added to adjust pH.

+ One new ampule should be used each day. Each ampule of TYVASO (once opened and transferred to the
  medicine cup) should remain in the device for no more than 1 day. Any remaining TYVASO and the medicine
  cup should be discarded at the end of each day.
+ Once a foil pouch is opened, use ampules within 7 days.
+ Store unused ampules of TYVASO in the foil pouch until use, protected from light.
+ Store at 25°C (77°F); excursions permitted to 15°C to 30°C (59°F to 86°F) [see USP Controlled Room Temperature].

Institutional Starter Kit For Single Patient Use Only.
Keep out of the reach of children.
NDC 66302-206-04
Rx only

Manufactured by United Therapeutics Corporation
Research Triangle Park, NC 27709

United
Therapeutics
CORPORATION

102130
Rev. 01/2024